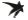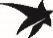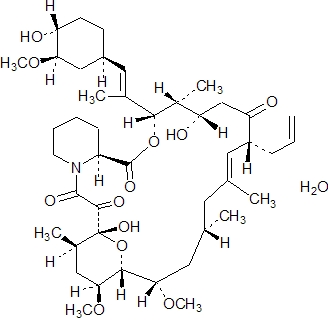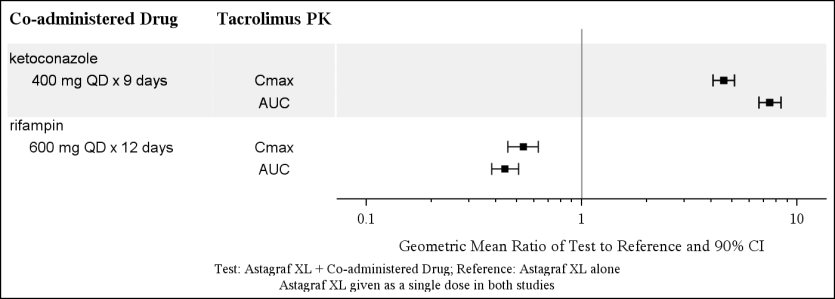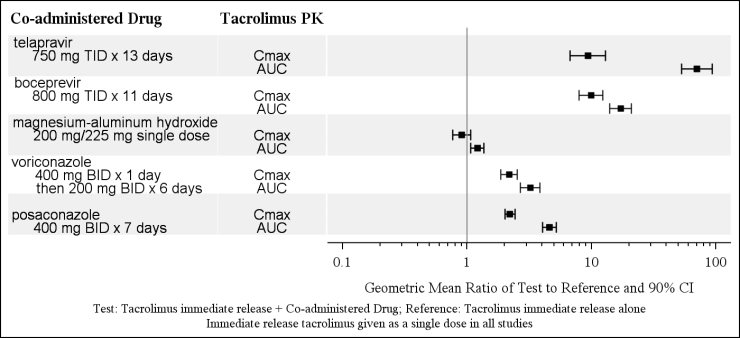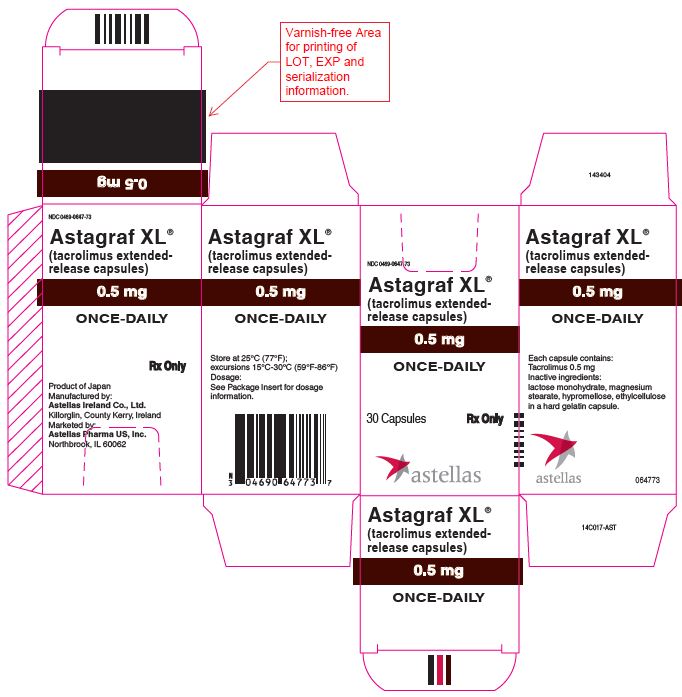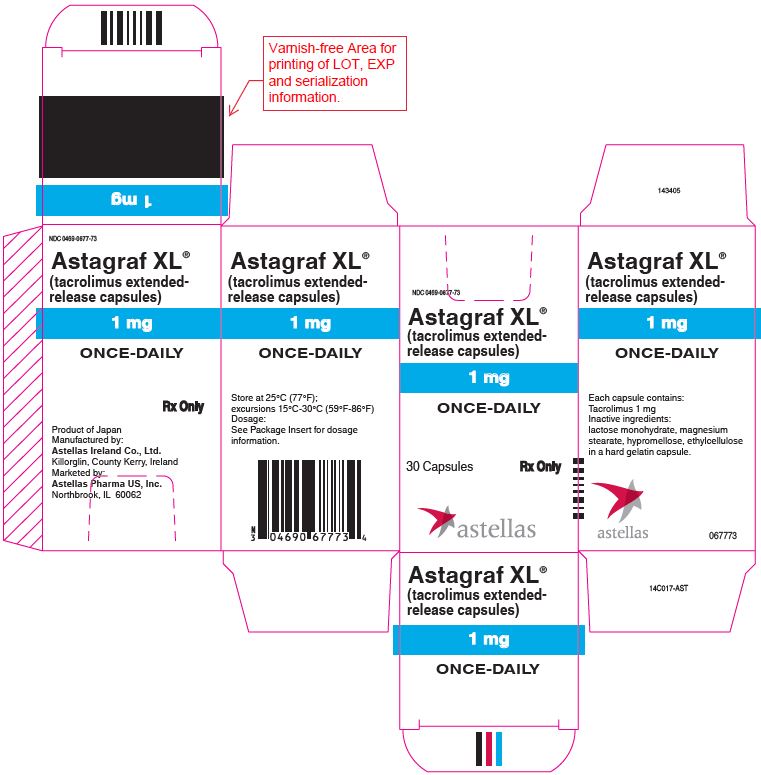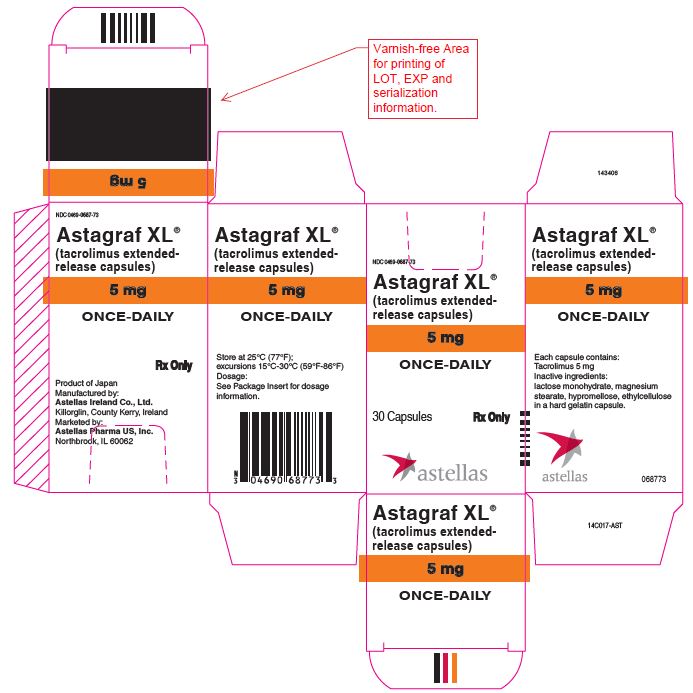 DRUG LABEL: ASTAGRAF XL
NDC: 0469-0647 | Form: CAPSULE, COATED, EXTENDED RELEASE
Manufacturer: Astellas Pharma US, Inc.
Category: prescription | Type: HUMAN PRESCRIPTION DRUG LABEL
Date: 20260114

ACTIVE INGREDIENTS: TACROLIMUS 0.5 mg/1 1

HIGHLIGHTS OF PRESCRIBING INFORMATION

These highlights do not include all the information needed to use ASTAGRAF XL® safely and effectively. See full prescribing information for ASTAGRAF XL.
ASTAGRAF XL (tacrolimus extended-release capsules), for oral use
Initial U.S. Approval: 1994

RECENT MAJOR CHANGES

Warnings and Precautions (5.6, 5.14) 11/2022

Warnings and Precautions, Cannabidiol Drug Interactions (5.15) 08/2023

WARNING: MALIGNANCIES AND SERIOUS INFECTIONS IN TRANSPLANT PATIENTS; AND INCREASED MORTALITY IN FEMALE LIVER TRANSPLANT PATIENTS

See full prescribing information for complete boxed warning.

- Increased risk for developing serious infections and malignancies with ASTAGRAF XL or other immunosuppressants that may lead to hospitalization or death. (5.1, 5.2)
- Increased mortality in female liver transplant patients with ASTAGRAF XL. Not approved for use in liver transplantation. (5.3)

1 INDICATIONS AND USAGE

ASTAGRAF XL is a calcineurin-inhibitor immunosuppressant indicated for the prophylaxis of organ rejection in kidney transplant patients in combination with other immunosuppressants in adult and pediatric patients who can swallow capsules intact. (1, 8.4, 14.1, 14.2)

2 DOSAGE AND ADMINISTRATION

- Capsules must be taken whole. (2.1)
- Take consistently every morning at the same time on an empty stomach at least 1 hour before a meal or at least 2 hours after a meal. (2.1)
- Avoid eating grapefruit or drinking grapefruit juice or alcohol. (2.1)
- African-American patients and patients with severe hepatic impairment may require dosing adjustments. (2.3)
- Frequent monitoring of trough concentrations is recommended. (2.4)
- For complete dosing information, see Full Prescribing Information.

Recommended ASTAGRAF XL Initial Dosage
Patient Population | Initial Oral Dosage | Whole Blood Trough Concentration Range
ADULT
With basiliximab, MMF and steroids | 0.15 to 0.2 mg/kg once daily prior to reperfusion or within 48 hours of completion of transplant | - Month 1: 7‑15 ng/mL - Months 2-6: 5‑15 ng/mL - > 6 Months: 5‑10 ng/mL
With MMF and steroids, without basiliximab induction | - First dose (pre-operative): 0.1 mg/kg, within 12 hours prior to reperfusion - Subsequent doses (post-operative): 0.2 mg/kg once daily at least 4 hours after pre-operative dose and within 12 hours after reperfusion | - Month 1: 10‑15 ng/mL - Months 2-6: 5‑15 ng/mL - > 6 Months: 5‑10 ng/mL
PEDIATRIC
With basiliximab, MMF and steroids | 0.3 mg/kg once daily, administered within 24 hours following reperfusion | - Month 1: 10‑20 ng/mL - > Month 1: 5‑15 ng/mL
MMF = Mycophenolate mofetil

3 DOSAGE FORMS AND STRENGTHS

Capsules: 0.5 mg, 1 mg, 5 mg (3)

4 CONTRAINDICATIONS

Known hypersensitivity to tacrolimus. (4)

5 WARNINGS AND PRECAUTIONS

- Not Interchangeable with Other Tacrolimus Products-Medication Errors: Instruct patients or caregivers to recognize the appearance of ASTAGRAF XL capsules. (5.4)
- New onset diabetes after transplant: Monitor blood glucose. (5.5)
- Nephrotoxicity (acute and/or chronic): May occur due to ASTAGRAF XL, drug interactions, concomitant nephrotoxic drugs. Monitor renal function; consider dosage reduction. (5.6)
- Neurotoxicity: Including risk of posterior reversible encephalopathy syndrome (PRES), monitor for neurologic abnormalities; reduce dosage or discontinue ASTAGRAF XL. (5.7)
- Hyperkalemia: Risk may be increased with other agents associated with hyperkalemia; monitor serum potassium levels. (5.8)
- Hypertension: May require antihypertensive therapy; monitor relevant drug interactions. (5.9)
- QT prolongation: Consider obtaining electrocardiograms and monitoring electrolytes in patients at high risk. (5.11)
- Immunizations: Avoid live vaccines. (5.12)
- Pure red cell aplasia: Consider discontinuation of ASTAGRAF XL. (5.13)
- Thrombotic Microangiopathy, Including Hemolytic Uremic Syndrome and Thrombotic Thrombocytopenic Purpura: May occur, especially in patients with infections and certain concomitant medications. (5.14)

6 ADVERSE REACTIONS

The most common adverse reactions (≥ 30%) are: diarrhea, constipation, nausea, peripheral edema, tremor and anemia. (6.1)

To report SUSPECTED ADVERSE REACTIONS, contact Astellas Pharma US, Inc. at 1-800-727-7003 or FDA at 1-800-FDA-1088 or www.fda.gov/medwatch.

7 DRUG INTERACTIONS

- Risk of rejection with strong CYP3A inducers and risk of serious adverse reactions with strong CYP3A inhibitors: Adjust dose and monitor tacrolimus concentrations. (2.4, 5.10, 7.2)
- Therapeutic drug monitoring and dose reduction for ASTAGRAF XL should be considered when ASTAGRAF XL is co-administered with cannabidiol (2.4, 5.15, 7.3).
- See Full Prescribing Information for clinically significant drug interactions. (7.1, 7.2, 7.3)

8 USE IN SPECIFIC POPULATIONS

Pregnancy: Can cause fetal harm. Advise pregnant women of the potential risk to the fetus. (8.1, 8.3)

FULL PRESCRIBING INFORMATION

WARNING: MALIGNANCIES AND SERIOUS INFECTIONS IN TRANSPLANT PATIENTS; AND INCREASED MORTALITY IN FEMALE LIVER TRANSPLANT PATIENTS

- Increased risk for developing serious infections and malignancies with ASTAGRAF XL® or other immunosuppressants that may lead to hospitalization or death. [see Warnings and Precautions (5.1, 5.2)]
- Increased mortality in female liver transplant patients with ASTAGRAF XL. ASTAGRAF XL is not approved for use in liver transplantation. [see Warnings and Precautions (5.3)]

1 INDICATIONS AND USAGE

ASTAGRAF XL® is indicated for the prophylaxis of organ rejection in kidney transplant patients in combination with other immunosuppressants in adult and pediatric patients who can swallow capsules intact [see Use in Specific Populations (8.4) and Clinical Studies (14.1), (14.2)].

2 DOSAGE AND ADMINISTRATION

2.1 Important Administration Instructions

- ASTAGRAF XL should not be used without the supervision by a physician with experience in immunosuppressive therapy.
- ASTAGRAF XL (tacrolimus extended-release capsules) is not interchangeable or substitutable for tacrolimus extended-release tablets, tacrolimus immediate-release capsules or tacrolimus for oral suspension. Under or overexposure to tacrolimus may result in graft rejection or other serious adverse reactions. Changes between tacrolimus immediate-release and extended-release dosage forms must occur under physician supervision [see Warnings and Precautions (5.4)].
- Advise patients to swallow ASTAGRAF XL capsules whole with liquid; patients must not chew, divide, or crush the capsules.
- ASTAGRAF XL should be taken consistently every morning at the same time to ensure consistent and maximum possible drug exposure, on an empty stomach at least 1 hour before a meal, or at least 2 hours after a meal [see Clinical Pharmacology (12.3)].
- If a dose is missed, the dose may be taken up to 14 hours after the scheduled time (i.e., for a missed 8:00 AM dose, a dose may be taken by 10:00 PM). Beyond the 14-hour time frame, the patient should wait until the usual scheduled time the following morning to take the next regular daily dose. Instruct the patient not to double the next dose.
- Advise patients to avoid eating grapefruit or drinking grapefruit juice or alcoholic beverages while taking ASTAGRAF XL [see Drug Interactions (7.2)].
- Therapeutic drug monitoring is recommended for all patients receiving ASTAGRAF XL [see Dosage and Administration (2.4)].

2.2 Dosage Recommendations for Kidney Transplant Patients

Table 1 includes the recommended starting ASTAGRAF XL dosages and whole blood trough concentration ranges; the observed trough concentrations are shown in another section of the Full Prescribing Information [see Clinical Studies (14)]. Titrate the ASTAGRAF XL dosage based on clinical assessments of rejection and tolerability, and to achieve target trough concentration ranges [see Dosage and Administration (2.4) and Warnings and Precautions (5.6, 5.7, 5.10, 5.11)].

Table 1: Recommended Starting Daily Dosage Regimen of ASTAGRAF XL
Recommended ASTAGRAF XL Initial Dosage*
Patient Population | Initial Oral Dosage | Whole Blood Trough Concentration Range
ADULT
With basiliximab, MMF and steroids | 0.15 to 0.2 mg/kg once daily prior to reperfusion or within 48 hours of completion of transplant | • Month 1: 7-15 ng/mL; • Months 2-6: 5-15 ng/mL; • > 6 Months: 5-10 ng/mL
With MMF and steroids, without basiliximab induction | • First dose (pre-operative): 0.1 mg/kg, within 12 hours prior to reperfusion; • Subsequent doses (post-operative): 0.2 mg/kg once daily at least 4 hours after pre-operative dose and within 12 hours after reperfusion | • Month 1: 10-15 ng/mL; • Months 2-6: 5-15 ng/mL; • > 6 Months: 5-10 ng/mL
PEDIATRIC
With basiliximab, MMF and steroids | 0.3 mg/kg once daily, administered within 24 hours following reperfusion. | • Month 1: 10-20 ng/mL; • > Month 1: 5-15 ng/mL
MMF = mycophenolate mofetil

2.3 Dosage Modifications for African-American Patients, Patients with Hepatic Impairment, and Drug Interactions

African-American patients, compared to Caucasian patients, may need to be titrated to higher ASTAGRAF XL dosages to attain comparable trough concentrations [see Clinical Pharmacology (12.3) and Clinical Studies (14)].

Patients with severe hepatic impairment (Child-Pugh ≥ 10) may require a lower starting dosage of ASTAGRAF XL, due to the reduced clearance and prolonged half-life [see Clinical Pharmacology (12.3)].

Dose adjustments of ASTAGRAF XL may be necessary when administered concomitantly with CYP3A inducers or CYP3A inhibitors or cannabidiol [see Warnings and Precautions (5.10, 5.15) and Drug Interactions (7.2, 7.3)].

2.4 Therapeutic Drug Monitoring

Measure tacrolimus whole blood trough concentrations at least two times on separate days during the first week after initiation of dosing and after a change in dosage, after a change in co-administration of CYP3A4 inducers and/or inhibitors or cannabidiol [see Drug Interactions (7.2, 7.3)], or after a change in renal or hepatic function. When interpreting measured concentrations, consider that the time to achieve tacrolimus steady state is approximately 7 days after initiating or changing the ASTAGRAF XL dose.

Monitor tacrolimus whole blood trough concentrations using a validated assay [e.g., immunoassays or high performance liquid chromatography with tandem mass spectrometric detection (HPLC/MS/MS)]. The immunosuppressive activity of tacrolimus is mainly due to the parent drug rather than to its metabolites. Immunoassays may react with metabolites as well as the parent drug. Therefore, whole blood tacrolimus trough concentrations obtained with immunoassays may be numerically higher than concentrations obtained with an assay using HPLC/MS/MS. Comparison of the whole blood tacrolimus trough concentrations of patients to those described in the prescribing information and other published literature must be made with knowledge of the assay method(s) employed.

3 DOSAGE FORMS AND STRENGTHS

ASTAGRAF XL CAPSULES:

• 0.5 mg: light yellow cap and orange body branded with red “ 647” on the capsule body and “0.5 mg” on the capsule cap.

• 1 mg: white cap and orange body branded with red “ 677” on the capsule body and “1 mg” on the capsule cap.

• 5 mg: grayish-red cap and orange body branded with red “ 687” on the capsule body and “5 mg” on the capsule cap.

4 CONTRAINDICATIONS

ASTAGRAF XL is contraindicated in patients with known hypersensitivity to tacrolimus [see Adverse Reactions (6.2)].

5 WARNINGS AND PRECAUTIONS

5.1 Lymphoma and Other Malignancies

Immunosuppressants, including ASTAGRAF XL, increase the risk of developing lymphomas and other malignancies, particularly of the skin. The risk appears to be related to the intensity and duration of immunosuppression rather than to the use of any specific agent. Examine patients for skin changes and advise to avoid or limit exposure to sunlight and UV light by wearing protective clothing and using a broad-spectrum sunscreen with a high protection factor.

Post-transplant lymphoproliferative disorder (PTLD), associated with Epstein-Barr Virus (EBV), has been reported in immunosuppressed organ transplant patients. The risk of PTLD appears greatest in patients who are EBV seronegative, a population which includes many young children. Monitor EBV serology during treatment.

5.2 Serious Infections

Immunosuppressants, including ASTAGRAF XL, increase the risk of developing bacterial, viral, fungal, and protozoal infections, including opportunistic infections. These infections may lead to serious, including fatal, outcomes. Serious viral infections reported include:

- Polyomavirus-associated nephropathy (especially due to BK virus infection)
- JC virus-associated progressive multifocal leukoencephalopathy (PML)
- Cytomegalovirus (CMV) infections: CMV seronegative transplant patients who receive an organ from a CMV seropositive donor are at highest risk of CMV viremia and CMV disease.

Monitor for the development of infection and adjust the immunosuppressive regimen to balance the risk of rejection with the risk of infection [see Adverse Reactions (6.1, 6.2)].

5.3 Increased Mortality in Female Liver Transplant Patients

In a clinical trial of 471 liver transplant patients randomized to ASTAGRAF XL or tacrolimus immediate-release product, mortality at 12 months was 10% higher among the 76 female patients (18%) treated with ASTAGRAF XL compared to the 64 female patients (8%) treated with tacrolimus immediate-release product. ASTAGRAF XL is not approved for the prophylaxis of organ rejection in patients who received a liver transplant.

5.4 Not Interchangeable with Other Tacrolimus Products - Medication Errors

Medication errors, including substitution and dispensing errors, between tacrolimus immediate-release products and ASTAGRAF XL (tacrolimus extended-release capsules) were reported outside the U.S. This led to serious adverse reactions, including graft rejection, or other adverse reactions due to under- or over-exposure to tacrolimus. ASTAGRAF XL is not interchangeable or substitutable for tacrolimus extended-release tablets, tacrolimus immediate-release capsules or tacrolimus for oral suspension. Changes between tacrolimus immediate-release and extended-release dosage forms must occur under physician supervision. Instruct patients and caregivers to recognize the appearance of ASTAGRAF XL capsules [see Dosage Forms and Strengths (3)] and to confirm with the healthcare provider if a different product is dispensed or if dosing instructions have changed.

5.5 New Onset Diabetes After Transplant

ASTAGRAF XL caused new onset diabetes after transplant (NODAT) in kidney transplant patients, which may be reversible in some patients. African-American and Hispanic kidney transplant patients are at an increased risk. Monitor blood glucose concentrations and treat appropriately [see Adverse Reactions (6.1) and Use in Specific Populations (8.8)].

5.6 Nephrotoxicity due to ASTAGRAF XL and Drug Interactions

ASTAGRAF XL, like other calcineurin-inhibitors, can cause acute or chronic nephrotoxicity in transplant patients due to its vasoconstrictive effect on renal vasculature, toxic tubulopathy and tubular-interstitial effects. Acute renal impairment associated with tacrolimus toxicity can result in high serum creatinine, hyperkalemia, decreased secretion of urea and hyperuricemia, and is usually reversible. In patients with elevated serum creatinine and tacrolimus whole blood trough concentrations greater than the recommended range, consider dosage reduction or temporary interruption of tacrolimus administration.

The risk for nephrotoxicity may increase when ASTAGRAF XL is concomitantly administered with CYP3A inhibitors (by increasing tacrolimus whole blood concentrations) or drugs associated with nephrotoxicity (e.g., aminoglycosides, ganciclovir, amphotericin B, cisplatin, nucleotide reverse transcriptase inhibitors, protease inhibitors). When tacrolimus is used concurrently with other known nephrotoxic drugs, monitor renal function and tacrolimus blood concentrations, and adjust dose of both tacrolimus and/or concomitant medications during concurrent use [see Adverse Reactions (6.1, 6.2) and Drug Interactions (7.2)].

5.7 Neurotoxicity

ASTAGRAF XL may cause a spectrum of neurotoxicities. The most severe neurotoxicities include posterior reversible encephalopathy syndrome (PRES), delirium, seizure and coma; others include tremors, paresthesias, headache, mental status changes, and changes in motor and sensory functions [see Adverse Reactions (6.1, 6.2)]. As symptoms may be associated with tacrolimus whole blood trough concentrations at or above the recommended range, monitor for neurologic symptoms and consider dosage reduction or discontinuation of ASTAGRAF XL if neurotoxicity occurs.

5.8 Hyperkalemia

Mild to severe hyperkalemia, which may require treatment, has been reported with tacrolimus including ASTAGRAF XL. Concomitant use of agents associated with hyperkalemia (e.g., potassium-sparing diuretics, ACE inhibitors, angiotensin receptor blockers) may increase the risk for hyperkalemia [see Adverse Reactions (6.1)]. Monitor serum potassium levels periodically during treatment.

5.9 Hypertension

Hypertension is a common adverse reaction of ASTAGRAF XL therapy and may require antihypertensive therapy [see Adverse Reactions (6.1)]. Some antihypertensive drugs can increase the risk for hyperkalemia [see Warnings and Precautions (5.8)]. Calcium-channel blocking agents may increase tacrolimus blood concentrations and require dosage reduction of ASTAGRAF XL [see Drug Interactions (7.2)].

5.10 Risk of Rejection with Strong CYP3A Inducers and Risk of Serious Adverse Reactions with Strong CYP3A Inhibitors

The concomitant use of strong CYP3A inducers may increase the metabolism of tacrolimus, leading to lower whole blood trough concentrations and greater risk of rejection. In contrast, the concomitant use of strong CYP3A inhibitors may decrease the metabolism of tacrolimus, leading to higher whole blood trough concentrations and greater risk of serious adverse reactions (e.g., neurotoxicity, QT prolongation) [see Warnings and Precautions (5.7, 5.11)]. Therefore, adjust ASTAGRAF XL dose and monitor tacrolimus whole blood trough concentrations when co-administering ASTAGRAF XL with strong CYP3A inhibitors (e.g., including, but not limited to, telaprevir, boceprevir, ritonavir, ketoconazole, itraconazole, voriconazole, clarithromycin) or strong CYP3A inducers (e.g., including, but not limited to, rifampin, rifabutin) [see Dosage and Administration (2.4) and Drug Interactions (7.2)]. A rapid, sharp rise in tacrolimus levels has been reported after co-administration with a strong CYP3A4 inhibitor, clarithromycin, despite an initial reduction of tacrolimus dose. Early and frequent monitoring of tacrolimus whole blood trough levels is recommended [see Drug Interactions (7.2)].

5.11 QT Prolongation

ASTAGRAF XL may prolong the QT/QTc interval and cause Torsades de pointes. Avoid ASTAGRAF XL in patients with congenital long QT syndrome. Consider obtaining electrocardiograms and monitoring electrolytes (magnesium, potassium, calcium) periodically during treatment in patients with congestive heart failure, bradyarrhythmias, those taking certain antiarrhythmic medications or other products that lead to QT prolongation, and those with electrolyte disturbances (e.g., hypokalemia, hypocalcemia, or hypomagnesemia).

When co-administering ASTAGRAF XL with other substrates and/or inhibitors of CYP3A, especially those that also have the potential to prolong the QT interval, a reduction in ASTAGRAF XL dosage, monitoring of tacrolimus whole blood concentrations, and monitoring for QT prolongation is recommended [see Dosage and Administration (2.4) and Drug Interactions (7.2)].

5.12 Immunizations

Whenever possible, administer the complete complement of vaccines before transplantation and treatment with ASTAGRAF XL.

Avoid the use of live attenuated vaccines during treatment with ASTAGRAF XL (e.g., intranasal influenza, measles, mumps, rubella, oral polio, BCG, yellow fever, varicella, and TY21a typhoid vaccines).

Inactivated vaccines noted to be safe for administration after transplantation may not be sufficiently immunogenic during treatment with ASTAGRAF XL.

5.13 Pure Red Cell Aplasia

Cases of pure red cell aplasia (PRCA) have been reported in patients treated with tacrolimus. All of these patients reported risk factors for PRCA such as parvovirus B19 infection, underlying disease, or concomitant medications associated with PRCA. A mechanism for tacrolimus-induced PRCA has not been elucidated. If PRCA is diagnosed, consider discontinuation of ASTAGRAF XL.

5.14 Thrombotic Microangiopathy (TMA) Including Hemolytic Uremic Syndrome and Thrombotic Thrombocytopenic Purpura

Cases of thrombotic microangiopathy (TMA), including hemolytic uremic syndrome (HUS) and thrombotic thrombocytopenic purpura (TTP), have been reported in patients treated with ASTAGRAF XL TMA may have a multifactorial etiology. Risk factors for TMA that can occur in transplant patients include, for example, severe infections, graft-versus-host disease (GVHD), Human Leukocyte Antigen (HLA) mismatch, the use of calcineurin inhibitors and mammalian target of rapamycin (mTOR) inhibitors. These risk factors may, either alone or combined, contribute to the risk of TMA.

In patients with signs and symptoms of TMA, consider tacrolimus as a risk factor. Concurrent use of tacrolimus and mTOR inhibitors may contribute to the risk of TMA.

5.15 Cannabidiol Drug Interactions

When cannabidiol and ASTAGRAF XL are co-administered, closely monitor for an increase in tacrolimus blood levels and for adverse reactions suggestive of tacrolimus toxicity. A dose reduction of ASTAGRAF XL should be considered as needed when ASTAGRAF XL is co-administered with cannabidiol [see Dosage and Administration (2.4) and Drug Interactions (7.3)].

6 ADVERSE REACTIONS

The following clinically significant adverse drug reactions are discussed in greater detail in other sections of labeling:

- Lymphoma and Other Malignancies [see Warnings and Precautions (5.1)]
- Serious Infections [see Warnings and Precautions (5.2)]
- Increased Mortality in Female Liver Transplant Patients [see Warnings and Precautions (5.3)]
- New Onset Diabetes after Transplant [see Warnings and Precautions (5.5)]
- Nephrotoxicity due to ASTAGRAF XL and Drug Interactions [see Warnings and Precautions (5.6)]
- Neurotoxicity [see Warnings and Precautions (5.7)]
- Hyperkalemia [see Warnings and Precautions (5.8)]
- Hypertension [see Warnings and Precautions (5.9)]
- QT Prolongation [see Warnings and Precautions (5.11)]
- Pure Red Cell Aplasia [see Warnings and Precautions (5.13)]
- Thrombotic Microangiopathy, Including Hemolytic Uremic Syndrome and Thrombotic Thrombocytopenic Purpura [see Warnings and Precautions (5.14)]

6.1 Clinical Studies Experience

Because clinical trials are conducted under widely varying conditions, adverse reaction rates observed in the clinical trials of a drug cannot be directly compared to rates in the clinical trials of another drug and may not reflect the rates observed in practice. In addition, the clinical trials were not designed to establish comparative differences across study arms with regards to the adverse reactions discussed below.

Kidney transplant patients were treated with ASTAGRAF XL (N=214) or tacrolimus immediate-release product (N=212) and concomitant immunosuppressants (median duration of exposure of 12 months) in a randomized, open-label, active-controlled trial of mostly U.S. patients (Study 1) [see Clinical Studies (14.1)]. The types of adverse reactions seen in Study 1 were similar to the adverse reactions seen in Study 2 [non-U.S. trial in kidney transplant patients treated with ASTAGRAF XL (N=331) or tacrolimus immediate-release product (N=336) and concomitant immunosuppressants] [see Clinical Studies (14.2)].

In Study 1, the proportion of patients who discontinued treatment due to adverse reactions was 9% and 11% in the ASTAGRAF XL and tacrolimus immediate-release treatment groups, respectively, through 12 months of treatment. The most common adverse reactions leading to discontinuation in ASTAGRAF XL-treated patients were related to infections or renal/urinary disorders.

Infections
The overall incidence of infections, serious infections, and infections with identified etiology reported in patients treated with the ASTAGRAF XL or tacrolimus immediate-release product in Study 1 are shown in Table 2.

Table 2: Percentage of Patients with Infections in Study 1a Through One Year Post-Kidney Transplant
 | ASTAGRAF XL, MMF, steroids, basiliximab; induction N=214 | Tacrolimus immediate-release; product, MMF, steroids, basiliximab induction; N=212
All Infections | 69% | 69%
Respiratory Infections | 34% | 31%
Urinary Tract Infections | 16% | 25%
Cytomegalovirus Infections | 10% | 11%
Bacterial Infections | 8% | 12%
Gastroenteritis | 7% | 3%
Polyomavirus Infections | 3% | 5%
Serious Infections | 22% | 23%
a Study 1 was not designed to support comparative claims of ASTAGRAF XL compared to tacrolimus immediate-release product for the adverse reactions reported in this table.

New Onset Diabetes After Transplant (NODAT)
The incidence of new onset diabetes after transplantation (defined by the composite occurrence of ≥ 2 fasting plasma glucose values that were > 126 mg/dL at ≥ 30 days apart, insulin use for ≥ 30 consecutive days, oral hypoglycemic use for ≥ 30 consecutive days, and/or HbA1C ≥ 6.5%) is summarized in Table 3 below for Study 1 through one year post-transplant [see Warnings and Precautions (5.5)].

Table 3: Percentage of Patients with NODAT Through One Year Post-Kidney Transplant in Study 1a
 | ASTAGRAF XL, MMF, steroids, basiliximab induction N=162 | Tacrolimus immediate-release product, MMF, steroids, basiliximab induction N=151
Composite NODAT | 36% | 35%
≥ 2 Fasting Plasma Glucose Values; ≥ 126 mg/dL ≥ 30 days apart | 26% | 23%
HbA1C ≥ 6.5% | 19% | 22%
Oral hypoglycemic use ≥ 30 consecutive days | 14% | 9%
Insulin use ≥ 30 consecutive days | 6% | 8%
a Study 1 was not designed to support comparative claims of ASTAGRAF XL compared to tacrolimus immediate-release product for the adverse reactions reported in this table.

Hyperkalemia
In Study 1 [see Clinical Studies (14.1)], 73 of 214 (34.1%) patients on ASTAGRAF XL had a serum potassium level greater than 5.4 up to 6.4 mEq/L, and 8 out of 214 (3.7%) patients had a serum potassium level greater than 6.4 mEq/L [see Warnings and Precautions (5.8)].

Common Adverse Reactions
The most common (≥ 30%) adverse reactions observed with ASTAGRAF XL in Study 1 were: diarrhea, constipation, nausea, peripheral edema, tremor, and anemia. The incidence of adverse reactions that occurred in ≥ 15% of ASTAGRAF XL-treated patients compared to tacrolimus immediate-release product through one year of treatment in Study 1 is shown by treatment groups in Table 4.

Table 4: Adverse Reactions (≥ 15%) in Kidney Transplant Patients Through One Year Post-Transplant in Study 1a
 | ASTAGRAF XL, MMF, steroids, basiliximab induction N=214 | Tacrolimus immediate-release product, MMF, steroids, basiliximab induction N=212
Diarrhea | 45% | 44%
Constipation | 40% | 32%
Nausea | 36% | 35%
Peripheral Edema | 36% | 34%
Tremor | 35% | 34%
Anemia | 33% | 29%
Hypertension | 28% | 30%
Vomiting | 25% | 25%
Hypomagnesemia | 24% | 27%
Insomnia | 24% | 28%
Hypophosphatemia | 23% | 28%
Headache | 22% | 24%
Hyperkalemia | 20% | 23%
Increased Blood Creatinine | 19% | 23%
Fatigue | 16% | 10%
Leukopenia | 16% | 16%
Hyperlipidemia | 16% | 17%
Hyperglycemia | 16% | 18%
a Study 1 was not designed to support comparative claims of ASTAGRAF XL compared to tacrolimus immediate-release for the adverse reactions reported in this table.

Less Frequently Reported Adverse Reactions (< 15% in ASTAGRAF XL-treated patients) by System Organ Class

The following adverse reactions were reported in clinical studies of kidney transplant patients who were treated with ASTAGRAF XL, MMF, and steroids (Studies 1 and 2):

- Blood and Lymphatic System Disorders: Hemolytic anemia, leukocytosis, neutropenia, thrombocytopenia, thrombotic microangiopathy
- Cardiac Disorders: Atrial fibrillation, atrial flutter, tachycardia
- Ear Disorders: Tinnitus
- Eye Disorders: Vision blurred, conjunctivitis
- Gastrointestinal Disorders: Abdominal distension, abdominal pain, aphthous stomatitis, dyspepsia, esophagitis, flatulence, gastritis, gastroesophageal reflux disease
- General Disorders and Administration Site Conditions: Anasarca, asthenia, edema, pyrexia
- Hepatobiliary Disorders: Abnormal hepatic function, cholestasis, hepatitis (acute and chronic), hepatotoxicity
- Infections and Infestations: Condyloma acuminatum, tinea versicolor
- Injury: Fall
- Investigations: Increased blood lactate dehydrogenase, increased blood urea, increased hepatic enzyme
- Metabolism and Nutrition Disorders: Anorexia, hyperphosphatemia, hyperuricemia, hypokalemia, hyponatremia, metabolic acidosis
- Musculoskeletal and Connective Tissue Disorders: Arthralgia, osteopenia, osteoporosis
- Neoplasms: Kaposi’s sarcoma
- Nervous System Disorders: Convulsion, dizziness, hypoesthesia, neurotoxicity, paresthesia, peripheral neuropathy
- Psychiatric Disorders: Agitation, anxiety, confusional state, depression, hallucination, mood swings, nightmare
- Renal and Urinary Disorders: Anuria, oliguria, proteinuria, renal failure, renal tubular necrosis, toxic nephropathy
- Respiratory, Thoracic and Mediastinal Disorders: Acute respiratory distress syndrome, dyspnea, pulmonary edema, productive cough
- Skin and Subcutaneous Tissue Disorders: Acne, alopecia, dermatitis, hyperhidrosis, hypotrichosis, pruritus, rash
- Vascular Disorders: Deep vein thrombosis, flushing

Pediatrics

De Novo Pediatric Transplant Patients

A study was conducted in 44 de novo pediatric transplant patients (including 25 kidney transplant patients; 13 randomized to ASTAGRAF XL and 12 randomized to Prograf), who were started on 0.3 mg/kg daily of tacrolimus product, given once daily for ASTAGRAF XL and divided into two doses for Prograf. Two kidney transplant patients on Prograf discontinued the study (withdrawn consent, sapovirus enteritis). Thirteen (13) pediatric kidney transplant patients completed 52 weeks on ASTAGRAF XL. The most common adverse reactions were diarrhea [7/13 (54%)], increased blood creatinine [6/13 (46%)], hypertension [3/13 (23%)], cough [4/13 (31%)], and upper respiratory tract infection [4/13 (31%)].

Stable Pediatric Transplant Patients

Another study was conducted in 81 stable pediatric allograft recipients (including 48 kidney transplant patients) 5 to 16 years of age converted 1:1 (mg:mg) from Prograf to ASTAGRAF XL. Seventy-six (76) pediatric patients completed at least one year of ASTAGRAF XL-based treatment. Treatment-related adverse reactions were reported in 35%, including 13% serious adverse reactions. The most frequent adverse reactions by system organ class were infections (55.7%), followed by gastrointestinal disorders (27.8%), skin and subcutaneous tissue disorders (21.5%), respiratory, thoracic and mediastinal disorders (20.3% each). The most common adverse reactions were diarrhea (13.9%), headache (13.9%) and cough (11.4%).

6.2 Postmarketing Experience

The following adverse reactions have been reported from marketing experience with tacrolimus in the U.S. and outside the U.S. Because these reactions are reported voluntarily from a population of uncertain size, it is not always possible to reliably estimate their frequency or establish a causal relationship to drug exposure. These reactions have been chosen for inclusion due to either their seriousness, frequency of reporting or causal connection to ASTAGRAF XL:

- Blood and Lymphatic System Disorders: Agranulocytosis, disseminated intravascular coagulation, hemolytic uremic syndrome, febrile neutropenia, pancytopenia, pure red cell aplasia [see Warnings and Precautions (5.13)], coagulopathy, thrombotic thrombocytopenic purpura, prolonged activated partial thromboplastin time, decreased blood fibrinogen
- Cardiac Disorders: Cardiac arrest, myocardial infarction, ventricular fibrillation, congestive cardiac failure, hypertrophic cardiomyopathy, pericardial effusion, angina pectoris, supraventricular extrasystoles, supraventricular tachycardia, bradycardia, Torsades de pointes, QT prolongation
- Ear Disorders: Hearing loss
- Eye Disorders: Blindness, optic neuropathy, optic atrophy, photophobia
- Gastrointestinal Disorders: Gastrointestinal hemorrhage, gastrointestinal perforation, pancreatitis, peritonitis, stomach ulcer, intestinal obstruction, ascites, colitis, ileus, impaired gastric emptying, dysphagia
- Hepatobiliary Disorders: Hepatic failure, hepatic necrosis, cirrhosis, cholangitis, venoocclusive liver disease, bile duct stenosis, hepatic steatosis, jaundice
- Hypersensitivity Reactions: Hypersensitivity, Stevens-Johnson syndrome, toxic epidermal necrolysis, urticaria
- Immune System Disorders: Graft versus host disease (acute and chronic)
- Investigations: Increased international normalized ratio
- Metabolism and Nutrition Disorders: Hypoproteinemia
- Musculoskeletal and Connective Tissue Disorders: Rhabdomyolysis, myalgia, polyarthritis, pain in extremity including Calcineurin-Inhibitor Induced Pain Syndrome (CIPS)
- Neoplasms: Lymphoma including EBV-associated lymphoproliferative disorder, hepatosplenic T-cell lymphoma, PTLD [see Warnings and Precautions (5.1)], leukemia, melanoma
- Nervous System Disorders: Cerebral infarction, progressive multifocal leukoencephalopathy (PML) sometimes fatal [see Warnings and Precautions (5.2)], posterior reversible encephalopathy syndrome (PRES) [see Warnings and Precautions (5.7)], coma, status epilepticus, quadriplegia, flaccid paralysis, hemiparesis, aphasia, syncope, carpal tunnel syndrome, nerve compression, mutism, dysarthria, somnolence
- Psychiatric Disorders: Mental status changes
- Renal and Urinary Disorders: Hemorrhagic cystitis, hematuria, urinary retention, urinary incontinence
- Respiratory, Thoracic and Mediastinal Disorders: Interstitial lung disease, pulmonary hypertension, lung infiltration, rhinitis allergic, hiccups
- Skin and Subcutaneous Tissue Disorders: Hyperpigmentation, photosensitivity
- Vascular Disorders: Hemorrhage

7 DRUG INTERACTIONS

7.1 Mycophenolic Acid

When ASTAGRAF XL is prescribed with a given dose of a mycophenolic acid (MPA) product, exposure to MPA is higher with ASTAGRAF XL co-administration than with cyclosporine co-administration with MPA, because cyclosporine interrupts the enterohepatic recirculation of MPA while tacrolimus does not. Monitor for MPA-associated adverse reactions and reduce the dose of concomitantly administered mycophenolic acid products as needed.

7.2 Effects of Other Drugs on ASTAGRAF XL

Table 5 displays the effects of other drugs on ASTAGRAF XL.

Table 5: Effects of Other Drugs/Substances on ASTAGRAF XLa
Drug/Substance Class or Name | Drug Interaction Effect | Recommendations
Grapefruit or grapefruit juiceb | May increase tacrolimus whole blood trough concentrations and increase the risk of serious adverse reactions (e.g., neurotoxicity, QT prolongation) [see Warnings and Precautions (5.7, 5.10, 5.11)]. | Avoid grapefruit or grapefruit juice.
Alcohol | May increase the rate of tacrolimus release and increase the risk of serious adverse reactions (e.g., neurotoxicity, QT prolongation) [see Warnings and Precautions (5.7, 5.10, 5.11)]. | Avoid alcoholic beverages.
Strong CYP3A Inducersc:; Antimycobacterials (e.g., rifampin, rifabutin), anticonvulsants (e.g., phenytoin, carbamazepine and phenobarbital), St John’s wort | May decrease tacrolimus whole blood trough concentrations and increase the risk of rejection [see Warnings and Precautions (5.10)]. | Increase ASTAGRAF XL dose and monitor tacrolimus whole blood trough concentrations [see Dosage and Administration (2.3, 2.4) and Clinical Pharmacology (12.3)].
Strong CYP3A Inhibitorsc:; Protease inhibitors (e.g., nelfinavir, telaprevir, boceprevir, ritonavir), azole antifungals (e.g., voriconazole, posaconazole, itraconazole, ketoconazole), antibiotics (e.g., clarithromycin, troleandomycin, chloramphenicol), nefazodone, letermovir, Schisandra sphenanthera extracts | May increase tacrolimus whole blood trough concentrations and increase the risk of serious adverse reactions (e.g., neurotoxicity, QT prolongation). A rapid, sharp rise in tacrolimus levels may occur early, despite an immediate reduction of tacrolimus dose [see Warnings and Precautions (5.7, 5.10, 5.11)]. | Reduce ASTAGRAF XL dose (for voriconazole and posaconazole, give one-third of the original dose) and adjust dose based on tacrolimus whole blood trough concentrations [see Dosage and Administration (2.3, 2.4) and Clinical Pharmacology (12.3)]. Early and frequent monitoring of tacrolimus whole blood trough levels should start within 1-3 days and continue monitoring as necessary [see Warnings and Precautions (5.10)].
Mild or Moderate CYP3A Inhibitors:; Clotrimazole, antibiotics (e.g., verapamil, diltiazem, nifedipine, nicardipine), amiodarone, danazol, ethinyl estradiol, cimetidine, lansoprazole and omeprazole | May increase tacrolimus whole blood trough concentrations and increase the risk of serious adverse reactions (e.g., neurotoxicity, QT prolongation) [see Warnings and Precautions (5.7, 5.10, 5.11)]. | Monitor tacrolimus whole blood trough concentrations and reduce ASTAGRAF XL dose if needed [see Dosage and Administration (2.3, 2.4) and Clinical Pharmacology (12.3)].
Other drugs, such as:; Magnesium and aluminum hydroxide antacids Metoclopramide | May increase tacrolimus whole blood trough concentrations and increase the risk of serious adverse reactions (e.g., neurotoxicity, QT prolongation) [see Warnings and Precautions (5.7, 5.10, 5.11)]. | Monitor tacrolimus whole blood trough concentrations and reduce ASTAGRAF XL dose if needed [see Dosage and Administration (2.3, 2.4) and Clinical Pharmacology (12.3)].
Mild or Moderate CYP3A Inducers; Methylprednisolone, prednisone | May decrease tacrolimus whole blood trough concentrations. | Monitor tacrolimus whole blood trough concentrations and adjust ASTAGRAF XL dose if needed [see Dosage and Administration (2.3, 2.4)].
Caspofungin | May decrease tacrolimus whole blood trough concentrations. | Monitor tacrolimus whole blood trough concentrations and adjust ASTAGRAF XL dose if needed [see Dosage and Administration (2.3, 2.4)].
a ASTAGRAF XL dosage adjustment recommendation based on observed effect of co-administered drug on tacrolimus exposures [see Clinical Pharmacology (12.3)], literature reports of altered tacrolimus exposures, or the other drug’s known CYP3A inhibitor/inducer status.
b High dose or double strength grapefruit juice is a strong CYP3A inhibitor; low dose or single strength grapefruit juice is a moderate CYP3A inhibitor.
c Strong CYP3A inhibitor/inducer, based on reported effect on exposures to tacrolimus along with supporting in vitro CYP3A inhibitor/inducer data, or based on drug-drug interaction studies with midazolam (sensitive CYP3A probe substrate).

Direct Acting Antiviral (DAA) Therapy

The pharmacokinetics of tacrolimus may be impacted by changes in liver function during DAA therapy, related to clearance of HCV virus. Close monitoring and potential dose adjustment of ASTAGRAF XL is warranted to ensure continued efficacy and safety [see Dosage and Administration (2.3, 2.4)].

7.3 Cannabidiol

The blood levels of tacrolimus may increase upon concomitant use with cannabidiol. When cannabidiol and ASTAGRAF XL are co-administered, closely monitor for an increase in tacrolimus blood levels and for adverse reactions suggestive of tacrolimus toxicity. A dose reduction of ASTAGRAF XL should be considered as needed when ASTAGRAF XL is co-administered with cannabidiol [see Dosage and Administration (2.4) and Warnings and Precautions (5.15)].

8 USE IN SPECIFIC POPULATIONS

8.1 Pregnancy

Pregnancy Exposure Registry

There is a pregnancy registry that monitors pregnancy outcomes in women exposed to ASTAGRAF XL during pregnancy. The Transplantation Pregnancy Registry International (TPRI) is a voluntary pregnancy exposure registry that monitors outcomes of pregnancy in female transplant recipients and those fathered by male transplant recipients exposed to immunosuppressants including tacrolimus. Healthcare providers are encouraged to advise their patients to register by contacting the Transplantation Pregnancy Registry International at 1-877-955-6877 or https://www.transplantpregnancyregistry.org/.

Risk Summary

Tacrolimus can cause fetal harm when administered to a pregnant woman. Data from postmarketing surveillance and TPRI suggest that infants exposed to tacrolimus in utero are at a risk of prematurity, birth defects/congenital anomalies, low birth weight, and fetal distress [see Human Data]. Advise pregnant women of the potential risk to the fetus.

Administration of oral tacrolimus to pregnant rabbits and rats throughout the period of organogenesis was associated with maternal toxicity/lethality, and an increased incidence of abortion, malformation and embryofetal death at clinically relevant doses [0.5 the maximum recommended clinical dose (0.2 mg/kg/day), on a mg/m^2 basis]. Administration of oral tacrolimus to pregnant rats after organogenesis and throughout lactation produced maternal toxicity, effects on parturition, reduced pup viability and reduced pup weight at clinically relevant doses (0.8 the maximum recommended clinical dose, on a mg/m^2 basis). Administration of oral tacrolimus to rats prior to mating, and throughout gestation and lactation produced maternal toxicity/lethality, marked effects on parturition, embryofetal loss, malformations, and reduced pup viability at clinically relevant doses (0.8 times the maximum recommended clinical dose, on a mg/m^2 basis). Interventricular septal defects, hydronephrosis, craniofacial malformations and skeletal effects were observed in offspring that died [see Animal Data].

The background risk of major birth defects and miscarriage in the indicated population is unknown.

In the U.S. general population, the estimated background risk of major birth defects and miscarriage in clinically recognized pregnancies is 2 to 4% and 15 to 20%, respectively.

Clinical Considerations

Disease-Associated Maternal and/or Embryo-Fetal Risk

Risks during pregnancy are increased in organ transplant recipients. The risk of premature delivery following transplantation is increased. Pre-existing hypertension and diabetes confer additional risk to the pregnancy of an organ transplant recipient. Pre-gestational and gestational diabetes are associated with birth defects/congenital anomalies, hypertension, low birth weight and fetal death.

Cholestasis of pregnancy (COP) was reported in 7% of liver or liver-kidney (LK) transplant recipients, compared with approximately 1% of pregnancies in the general population. However, COP symptoms resolved postpartum and no long-term effects on the offspring were reported.

Maternal Adverse Reactions

ASTAGRAF XL may increase hyperglycemia in pregnant women with diabetes (including gestational diabetes). Monitor maternal blood glucose levels regularly [see Warnings and Precautions (5.5)].

ASTAGRAF XL may exacerbate hypertension in pregnant women and increase pre-eclampsia. Monitor and control blood pressure [see Warnings and Precautions (5.8, 5.9)].

Fetal/Neonatal Adverse Reactions

Renal dysfunction, transient neonatal hyperkalemia and low birth weight have been reported at the time of delivery in infants of mothers taking ASTAGRAF XL.

Labor or Delivery

There is an increased risk for premature delivery (< 37 weeks) following transplantation and maternal exposure to ASTAGRAF XL.

Data

Human Data
There are no adequate and well-controlled studies on the effects of tacrolimus in human pregnancy.

Safety data from the TPRI and postmarketing surveillance suggest infants exposed to tacrolimus in utero have an increased risk for miscarriage, pre-term delivery (< 37 weeks), low birth weight (< 2500 g), birth defects/congenital anomalies and fetal distress.

TPRI reported 450 and 241 total pregnancies in kidney and liver transplant recipients exposed to tacrolimus, respectively. The TPRI pregnancy outcomes are summarized in Table 6. In the table below, the number of recipients exposed to tacrolimus concomitantly with mycophenolic acid (MPA) products during the preconception and first trimester periods is high (27% and 29% for kidney and liver transplant recipients, respectively). Because MPA products may also cause birth defects, the birth defect rate may be confounded and this should be taken into consideration when reviewing the data, particularly for birth defects. Birth defects observed include cardiac malformations, craniofacial malformations, renal/urogenital disorders, skeletal abnormalities, neurological abnormalities and multiple malformations.

Table 6: TPRI-Reported Pregnancy Outcomes in Transplant Recipients with Exposure to Tacrolimus
 | Kidney | Liver
Pregnancy Outcomes [Includes multiple births and terminations.] | 462 | 253
Miscarriage | 24.5% | 25%
Live births | 331 | 180
Pre-term delivery (< 37 weeks) | 49% | 42%
Low birth weight (< 2500 g) | 42% | 30%
Birth defects | 8% [Birth defect rate confounded by concomitant MPA products exposure in over half of offspring with birth defects.] | 5%

Additional information reported by TPRI in pregnant transplant patients receiving tacrolimus included diabetes during pregnancy in 9% of kidney recipients and 13% of liver recipients and hypertension during pregnancy in 53% of kidney recipients and 16.2% of liver recipients.

Animal Data

Administration of oral tacrolimus to pregnant rabbits throughout organogenesis produced maternal toxicity and abortion at 0.32 mg/kg (0.5 times the maximum recommended clinical dose [0.2 mg/kg/day], on a mg/m^2 basis). At 1 mg/kg (1.6 times the maximum recommended clinical dose), embryofetal lethality and fetal malformations (ventricular hypoplasia, interventricular septal defect, bulbous aortic arch, stenosis of ductus arteriosus, omphalocele, gallbladder agenesis, skeletal anomalies) were observed. Administration of 3.2 mg/kg oral tacrolimus (2.6 times the maximum recommended clinical dose) to pregnant rats throughout organogenesis produced maternal toxicity/lethality, embryofetal lethality and decreased fetal body weight in the offspring of C-sectioned dams; and decreased pup viability and interventricular septal defect in offspring of dams that delivered.

In a peri-/postnatal development study, oral administration of tacrolimus to pregnant rats during late gestation (after organogenesis) and throughout lactation produced maternal toxicity, effects on parturition, and reduced pup viability at 3.2 mg/kg (2.6 times the maximum recommended clinical dose); among these pups that died early, an increased incidence of kidney hydronephrosis was observed. Reduced pup weight was observed at 1.0 mg/kg (0.8 times the maximum recommended clinical dose).

Administration of oral tacrolimus to rats prior to mating, and throughout gestation and lactation produced maternal toxicity/lethality, embryofetal loss and reduced pup viability at 3.2 mg/kg (2.6 times the maximum recommended clinical dose range). Interventricular septal defects, hydronephrosis, craniofacial malformations and skeletal effects were observed in offspring that died. Effects on parturition (incomplete delivery of nonviable pups) were observed at 1 mg/kg (0.8 times the maximum recommended clinical dose) [see Nonclinical Toxicology (13.1)].

8.2 Lactation

Risk Summary
Controlled lactation studies have not been conducted in humans; however, tacrolimus has been reported to be present in human milk. The effects of tacrolimus on the breastfed infant, or on milk production, have not been assessed. Tacrolimus is excreted in rat milk and in peri-/postnatal rat studies; exposure to tacrolimus during the postnatal period was associated with developmental toxicity in the offspring at clinically relevant doses [see Pregnancy (8.1) and Nonclinical Toxicology (13.1)].

The developmental and health benefits of breastfeeding should be considered along with the mother’s clinical need for ASTAGRAF XL and any potential adverse effects on the breastfed child from ASTAGRAF XL or from the underlying maternal condition.

8.3 Females and Males of Reproductive Potential

Contraception
ASTAGRAF XL can cause fetal harm when administered to pregnant women. Advise female and male patients of reproductive potential to speak to their healthcare provider on family planning options including appropriate contraception prior to starting treatment with ASTAGRAF XL [see Use in Specific Populations (8.1) and Nonclinical Toxicology (13.1)].

Infertility
Based on findings in animals, male and female fertility may be compromised by treatment with ASTAGRAF XL [see Nonclinical Toxicology (13.1)].

8.4 Pediatric Use

The safety and effectiveness of ASTAGRAF XL in de novo pediatric kidney transplant patients have been established. Use of ASTAGRAF XL in pediatric kidney transplant patients is based on adequate and well-controlled studies of ASTAGRAF XL in adult kidney transplant patients [see Clinical Studies (14.1, 14.2)] and supported by pharmacokinetic and safety data of ASTAGRAF XL in pediatric transplant patients 4 years of age and older who are able to swallow capsules intact and Prograf (tacrolimus) capsules in adult and pediatric transplant patients [see Clinical Pharmacology (12.3)].

De Novo Pediatric Kidney Transplant Patients
A pharmacokinetic and safety study included 25 de novo pediatric kidney transplant patients, 4 to 15 years of age, randomized to Prograf (N=12) or ASTAGRAF XL (N=13). Tacrolimus exposures for the two drug products were comparable on Days 7 and 28 [see Clinical Pharmacology (12.3)]. Among the 13 pediatric kidney transplant patients who completed 52 weeks on ASTAGRAF XL, there were no graft loss, deaths or episodes of biopsy-proven acute rejection [see Dosage and Administration (2.2) and Adverse Reactions (6.1)].

Stable Pediatric Kidney Transplant Patients
Another pharmacokinetic and safety study included 48 stable pediatric kidney transplant patients, 5 to 16 years of age, who were converted from a Prograf-based regimen to ASTAGRAF XL. Tacrolimus systemic exposures for the two drug products were comparable [see Clinical Pharmacology (12.3)]. Acute rejections were reported in 2/48 kidney pediatric patients that responded to subsequent treatment. There were no graft failures or deaths following use of ASTAGRAF XL during the 54-week follow up [see Adverse Reactions (6.1)].

8.5 Geriatric Use

Clinical studies of ASTAGRAF XL did not include sufficient numbers of patients aged 65 and over to determine whether they respond differently from younger patients. In Studies 1 and 2, 29 patients were 65 years of age and older, and 3 patients were 75 years of age and over [see Clinical Studies (14)]. Other reported clinical experience has not identified differences in responses between the elderly and younger patients. In general, dose selection for an elderly patient should be cautious, usually starting at the low end of the dosing range, reflecting the greater frequency of decreased hepatic, renal, or cardiac function, and of concomitant disease or other drug therapy.

8.6 Renal Impairment

The pharmacokinetics of tacrolimus in patients with renal impairment was similar to that in healthy subjects with normal renal function. However, due to its potential for nephrotoxicity, monitoring of renal function in patients with renal impairment is recommended; tacrolimus dosage should be reduced if indicated [see Warnings and Precautions (5.6) and Clinical Pharmacology (12.3)].

8.7 Hepatic Impairment

The mean clearance of tacrolimus was substantially lower in patients with severe hepatic impairment (mean Child-Pugh score: > 10) compared to healthy subjects with normal hepatic function [see Clinical Pharmacology (12.3)]. With greater tacrolimus whole blood trough concentrations in patients with severe hepatic impairment, there is a greater risk of adverse reactions and dosage reduction is recommended [see Dosage and Administration (2.3)]. For patients with moderate hepatic impairment, monitor tacrolimus whole blood trough concentrations. For patients with mild hepatic impairment, no dosage adjustments are needed.

8.8 Race or Ethnicity

African-American patients may need to be titrated to higher dosages to attain comparable trough concentrations compared to Caucasian patients [see Dosage and Administration (2.3), Clinical Pharmacology (12.3), and Clinical Studies (14)].

African-American and Hispanic patients are at increased risk for new onset diabetes after transplant. Monitor blood glucose concentrations and treat appropriately [see Warnings and Precautions (5.5)].

10 OVERDOSAGE

Postmarketing cases of overdose with tacrolimus have been reported. Overdosage adverse reactions included:

- nervous system disorders (tremor, headache, confusional state, balance disorders, encephalopathy, lethargy and somnolence)
- gastrointestinal disturbances (nausea, vomiting, and diarrhea)
- abnormal renal function (increased blood urea nitrogen and elevated serum creatinine)
- urticaria
- hypertension
- peripheral edema, and
- infections [one fatal postmarketing case of bilateral pneumopathy and CMV infection was attributed to tacrolimus (extended-release) overdose].

Based on the poor aqueous solubility and extensive erythrocyte and plasma protein binding, it is anticipated that tacrolimus is not dialyzable to any significant extent; there is no experience with charcoal hemoperfusion. The oral use of activated charcoal has been reported in treating acute overdoses, but experience has not been sufficient to warrant recommending its use. General supportive measures and treatment of specific symptoms should be followed in all cases of overdosage.

11 DESCRIPTION

Tacrolimus is the active ingredient in ASTAGRAF XL. Tacrolimus is a calcineurin-inhibitor immunosuppressant produced by Streptomyces tsukubaensis. Chemically, tacrolimus is designated as [3S – [3R*[E(1S*, 3S*, 4S*)], 4S*, 5R*, 8S*, 9E, 12R*, 14R*, 15S*, 16R*, 18S*, 19S*, 26aR*]] – 5, 6, 8, 11, 12, 13, 14, 15, 16, 17, 18, 19, 24, 25, 26, 26a – hexadecahydro – 5, 19 – dihydroxy – 3 – [2 – (4 – hydroxy – 3 – methoxycyclo – hexyl) – 1 – methylethenyl] – 14, 16 – dimethoxy – 4, 10, 12, 18 – tetramethyl – 8 – (2 – propenyl) – 15, 19 – epoxy – 3H – pyrido[2, 1 – c][1, 4]oxaazacyclotricosine – 1, 7, 20, 21(4H, 23H) – tetrone, monohydrate.

The chemical structure of tacrolimus is:

Tacrolimus has an empirical formula of C44H69NO12•H2O and a formula weight of 822.03. Tacrolimus appears as white crystals or crystalline powder. It is practically insoluble in water, freely soluble in ethanol, and very soluble in methanol and chloroform.

ASTAGRAF XL is available for oral administration as hard gelatin capsules (tacrolimus extended-release capsules) containing the equivalent of 0.5 mg, 1 mg or 5 mg of anhydrous tacrolimus, USP. Inactive ingredients include ethylcellulose NF, hypromellose USP, magnesium stearate NF and lactose monohydrate NF. The ingredients are directly proportional across all capsule strengths. The capsule shell contains gelatin NF, titanium dioxide USP, ferric oxide NF, and sodium lauryl sulfate.

12 CLINICAL PHARMACOLOGY

12.1 Mechanism of Action

Tacrolimus binds to an intracellular protein, FKBP-12. A complex of tacrolimus-FKBP-12, calcium, calmodulin, and calcineurin (a ubiquitous mammalian intracellular enzyme) is then formed and the phosphatase activity of calcineurin is inhibited. Such inhibition prevents the dephosphorylation and translocation of various factors such as the nuclear factor of activated T-cells (NF-AT), and nuclear factor kappa-light-chain-enhancer of activated B-cells (NF-κB).

Tacrolimus inhibits the expression and/or production of several cytokines that include interleukin (IL)-1 beta, IL‑2, IL-3, IL-4, IL-5, IL-6, IL-8, IL-10, gamma interferon, tumor necrosis factor-alpha, and granulocyte macrophage colony-stimulating factor. Tacrolimus also inhibits IL-2 receptor expression and nitric oxide release, induces apoptosis and production of transforming growth factor-beta that can lead to immunosuppressive activity. The net result is the inhibition of T-lymphocyte activation and proliferation as well as T-helper-cell-dependent B-cell response (i.e., immunosuppression).

12.3 Pharmacokinetics

Table 7 summarizes the pharmacokinetic (PK) parameters of tacrolimus following oral administration of ASTAGRAF XL in healthy subjects and in kidney transplant patients. Whole blood tacrolimus concentrations in these PK studies were measured using validated HPLC/MS/MS assays.

Table 7: Pharmacokinetic Parameters of ASTAGRAF XL (Given Once Daily) in Healthy Subjects and in Kidney Transplant Patients (Under Fasted Conditions)
Population | ASTAGRAF XL Dosea | Dayb | PK Parameters of ASTAGRAF XL
Population | ASTAGRAF XL Dosea | Dayb | Cmaxc; (ng/mL) | Tmaxd; (hr) | AUC24c; (ng•hr/mL) | C24f; (ng/mL)
Healthy Subjects; (N=24) | 4 mg; 4 mg | Day 1; Day 10 | 6.2 ± 2.1; 11.6 ± 3.4 | 2.0 [1.0-5.0]; 2.0 [1.0-3.0] | 74 ± 22; 155 ± 46 | 2.3 ± 0.8; 4.7 ± 1.5
Adult Kidney; De novoe (N=17) | 0.20 mg/kg; 0.19 mg/kg; 0.18 mg/kg; 0.18 mg/kg | Day 1; Day 3; Day 7; Day 14 | 26.0 ± 13.7; 31.0 ± 13.9; 32.2 ± 10.2; 32.7 ± 9.0 | 3.0 [2-24]; 2.0 [0.5-2.0]; 2.0 [1-6]; 2.0 [1-4] | 372 ± 202; 437 ± 175; 405 ± 117; 412 ± 109 | 12.1 ± 7.2; 13.5 ± 5.6; 11.4 ± 4.0; 11.2 ± 3.9
Adult Kidney (6 months or greater post-transplant) (N=60) | 5.2 mg/dayg | Day 14g | 16.1 ± 5.3 | 2.0 [1.0 - 6.0] | 222 ± 64 | 6.7 ± 1.9h
a Healthy adult subjects (actual administered dose of ASTAGRAF XL); adult de novo kidney transplant patients (actual group mean dose of ASTAGRAF XL).
b Day of ASTAGRAF XL treatment and PK profiling.
c Arithmetic means ± S.D.
d Median [range].
e “De novo” refers to immunosuppression starting at the time of transplantation; data from PK substudy of Study 2.
f Tacrolimus trough concentration before the next dose.
g Same daily dose of ASTAGRAF XL for 14-day period.
h Correlation coefficient of AUC24 to Cmin r = 0.88.

In de novo adult kidney transplant patients, the tacrolimus systemic exposure, as assessed by AUC24, for ASTAGRAF XL 0.2 mg/kg once daily on Day 1 post-transplant was 18% (Ratio [SD]: 0.822 [1.647]) lower when compared with Prograf (tacrolimus immediate-release) 0.2 mg/kg/day given twice daily. By Day 3 post-transplant, the AUC24 was similar between the two formulations. On Day 14 (steady state), the AUC24 for ASTAGRAF XL was 21% (Ratio [SD]: 1.207 [1.326]) higher than that of Prograf (tacrolimus immediate-release), at comparable trough concentrations (C24).

Due to intersubject variability in tacrolimus PK, individualization of dosing regimen is necessary for optimal therapy [see Dosage and Administration (2.3, 2.4)].

Pharmacokinetic data indicate that whole blood concentrations rather than plasma concentrations serve as the more appropriate sampling compartment to describe tacrolimus PK.

Absorption
In healthy subjects, the administration of escalating ASTAGRAF XL doses ranging from 1.5 mg to 10 mg resulted in dose-proportional increases in tacrolimus AUC and C24h, and no change in elimination half-life.

Food Effects
The presence of a meal affects the absorption of tacrolimus; the rate and extent of absorption is greatest under fasted conditions. In 24 healthy subjects, administration of ASTAGRAF XL immediately following a high-fat meal (150 protein calories, 250 carbohydrate calories, and 500 to 600 fat calories) reduced the Cmax, AUCt, and AUCinf of tacrolimus by approximately 25% compared with fasting values. Food delayed the median Tmax from 2 hours in the fasted state to 4 hours in the fed state; however, the terminal half-life remained 36 hours regardless of dosing conditions. The time when a meal is consumed also affected tacrolimus bioavailability. In 24 healthy subjects, when ASTAGRAF XL was administered 1.5 hours after consumption of a high-fat breakfast, tacrolimus exposure was decreased approximately 35%. Administration of ASTAGRAF XL 1 hour prior to a high-fat breakfast reduced tacrolimus exposure by 10%. ASTAGRAF XL capsules should be taken, preferably on an empty stomach, at least 1 hour before a meal or at least 2 hours after a meal.

Chronopharmacokinetic Effect
In 23 healthy subjects, a diurnal effect on the absorption of tacrolimus was observed. Evening dosing of ASTAGRAF XL reduced AUCinf by 35% relative to morning dosing. ASTAGRAF XL capsules should be taken consistently at the same time every morning.

Distribution
The plasma protein binding of tacrolimus is approximately 99% and is independent of concentration over a range of 5-50 ng/mL. Tacrolimus is bound mainly to albumin and alpha-1-acid glycoprotein, and has a high level of association with erythrocytes. The distribution of tacrolimus between whole blood and plasma depends on several factors, such as hematocrit, temperature at the time of plasma separation, drug concentration, and plasma protein concentration. In a U.S. trial in which tacrolimus was administered as tacrolimus immediate-release, the ratio of whole blood concentration to plasma concentration averaged 35 (range 12 to 67).

Elimination

Metabolism
The desired pharmacological activity of tacrolimus is primarily due to the parent drug. Tacrolimus is extensively metabolized by the mixed-function oxidase system, primarily the cytochrome P-450 system (CYP3A4 and CYP3A5). A metabolic pathway leading to the formation of 8 possible metabolites has been proposed. Demethylation and hydroxylation were identified as the primary mechanisms of biotransformation in vitro. The major metabolite identified in incubations with human liver microsomes is 13-demethyl tacrolimus. In in vitro studies, a 31-demethyl metabolite has been reported to have the same activity as tacrolimus.

Excretion
In a mass balance study of orally-administered radiolabeled tacrolimus to 6 healthy subjects, the mean recovery of the radiolabel was 94.9 ± 30.7%. Fecal elimination accounted for 92.6 ± 30.7% and urinary elimination accounted for 2.3 ± 1.1% of the total radiolabel administered. The elimination half-life based on radioactivity was 31.9 ± 10.5 hours, whereas it was 48.4 ± 12.3 hours based on tacrolimus concentrations. The mean clearance of radiolabel was 0.226 ± 0.116 L/hr/kg and the mean clearance of tacrolimus was 0.172 ± 0.088 L/hr/kg.

The elimination half-life of tacrolimus after oral administration of 4 mg ASTAGRAF XL daily for 10 days was 38 ± 3 hours in 24 healthy subjects.

Specific Populations

Pediatric Patients

De Novo Pediatric Transplant Patients
A PK study to compare ASTAGRAF XL to Prograf capsules was conducted in 44 de novo pediatric transplant patients, including 25 pediatric de novo kidney transplant patients, 4 to 15 years of age (mean age of 10.6 years). These patients were administered a starting daily dose of 0.3 mg/kg/day of Prograf capsules divided into two daily doses or ASTAGRAF XL once daily. Overall, the tacrolimus PK parameters AUC24 and C24 are comparable among Prograf and ASTAGRAF XL on Days 7 and 28 (Table 8).

Table 8: Tacrolimus Pharmacokinetic Parameters Following Daily Doses of Prograf Capsules or ASTAGRAF XL in Pediatric De Novo Kidney Transplant Patients 4 to 15 Years of Age
Study Visita | Mean ± SD (Range) PK Parameters for Prograf Capsules and ASTAGRAF XL
Study Visita | PK Parameters | Prograf Capsulesb (N=10) | ASTAGRAF XL (N=10)
Day 1 | AUC24 (ng∙hr/mL) | 280.4 ± 164.4; (145.0 – 688.4) | 211.4 ± 128.2; (76.9 – 459.8)
Day 1 | Cmax (ng/mL) | 23.1 ± 14.4; (8.2 – 55.7) | 17.7 ± 11.1; (5.0 – 44.9)
Day 1 | C24 (ng/mL)c | 8.5 ± 5.4; (3.2 – 16.7) | 6.7 ± 4.3; (2.0 – 16.5)
Day 1 | Tmax (hr)d | 2.0; (0.9 – 4.0) | 2.0; (1.0 – 12.0)
Day 7 | AUC24 (ng∙hr/mL) | 347.2 ± 124.2; (153.7 – 561.8) | 350.6 ± 92.7; (149.0 – 493.0)
Day 7 | Cmax (ng/mL) | 28.7 ± 14.6; (10.5 – 49.0) | 37.7 ± 13.9; (15.1 – 62.6)
Day 7 | C24 (ng/mL)c | 9.6 ± 2.8; (5.9 – 16.0) | 8.4 ± 2.7; (4.3 – 14.4)
Day 7 | Tmax (hr)d | 1.0; (1.0 – 2.3) | 1.0; (1.0 – 2.0)
Day 28 | AUC24 (ng∙hr/mL) | 323.6 ± 114.5; (234.5 – 614.0) | 322.4 ± 78.1; (240.3 – 516.4)
Day 28 | Cmax (ng/mL) | 28.5 ± 17.1; (17.5 – 70.1) | 24.7 ± 4.8; (14.2 – 32.5)
Day 28 | C24 (ng/mL)c | 9.8 ± 3.1; (5.4 – 16.0) | 9.2 ± 3.0; (5.1 – 15.9)
Day 28 | Tmax (hr)d | 1.0; (1.0 – 4.0) | 1.5; (1.0 – 4.0)
a Study Visit Day on which PK profiles were collected following administration of Prograf capsules or ASTAGRAF XL.
b PK estimates following the morning Prograf capsules dose are reported for Tmax and Cmax.
c Observed whole blood tacrolimus trough levels at 12 hours following the evening dose of Prograf capsules or 24 hours after the morning dose of ASTAGRAF XL.
d Tmax - Reported as median (range).

Stable Pediatric Transplant Patients
Another PK study to compare ASTAGRAF XL to Prograf capsules was conducted in 81 stable pediatric transplant patients, including 48 pediatric kidney transplant patients, 5 to 16 years of age (mean age of 11.0 years). Pediatric kidney transplant patients who had been administered Prograf for at least 3 months prior to treatment were converted on a 1:1 (mg:mg) basis from Prograf, given in two divided doses, to ASTAGRAF XL once-daily. Overall, the tacrolimus AUC24, Cmax, and C24 are comparable upon conversion from Prograf to ASTAGRAF XL on a 1:1 (mg:mg) basis in stable pediatric kidney transplant patients (Table 9).

Table 9: Tacrolimus Pharmacokinetic Parameters at Steady State Following 1:1 (mg:mg) Total Daily Dose Conversion from Prograf Capsules to ASTAGRAF XL in Stable Pediatric Kidney Transplant Patients 5 to 16 Years of Age
Organ Transplant; Population | Mean ± SD (Range) PK Parameters for Prograf Capsules and ASTAGRAF XL
Pediatric Kidney (N=45) | PK Parameters | Prograf Capsules | ASTAGRAF XL
Pediatric Kidney (N=45) | AUC24 (ng∙hr/mL) | 188.8 ± 53.5; (102.3 – 406.8) | 173.2 ± 44.6; (80.9 – 262.5)
Pediatric Kidney (N=45) | Cmax (ng/mL) | 14.9 ± 5.8; (4.9 – 34.4) | 12.5 ± 4.5; (5.4 – 24.4)
Pediatric Kidney (N=45) | C24a (ng/mL) | 5.6 ± 1.9; (2.9 – 13.8) | 5.1 ± 1.4; (2.0 – 8.4)

a Observed whole blood tacrolimus trough levels at 12 hours following the evening dose of Prograf capsules and at 24 hours after the morning dose of ASTAGRAF XL once daily under steady-state conditions.

Patients with Renal Impairment
Tacrolimus pharmacokinetics following a single administration of tacrolimus immediate-release injection (administered as a continuous IV infusion) were determined in 12 patients (7 not on dialysis and 5 on dialysis, serum creatinine of 3.9 ± 1.6 and 12.0 ± 2.4 mg/dL, respectively) prior to their kidney transplant. The mean clearance of tacrolimus in patients with renal dysfunction given tacrolimus IV was similar to that in healthy subjects given tacrolimus IV and in healthy subjects given oral tacrolimus immediate-release [see Use in Specific Populations (8.6)].

Patients with Hepatic Impairment
Tacrolimus pharmacokinetics have been determined in six patients with mild hepatic impairment (mean Child-Pugh score: 6.2) following single oral administration of tacrolimus immediate-release. The mean clearance of tacrolimus in patients with mild hepatic impairment was not substantially different from that in healthy subjects. Tacrolimus pharmacokinetics were studied in six patients with severe hepatic impairment (mean Child-Pugh score: > 10). The mean clearance was substantially lower in patients with severe hepatic impairment [see Dosage and Administration (2.3) and Use in Specific Populations (8.7)].

Racial or Ethnic Groups
The pharmacokinetics of tacrolimus was studied following single oral administration of tacrolimus immediate-release (5 mg) in 10 African-American, 12 Latino-American, and 12 Caucasian healthy subjects [see Dosage and Administration (2.2), Use in Specific Populations (8.8) and Clinical Studies (14)]:

- The mean (± SD) tacrolimus Cmax in African-Americans (23.6 ± 12.1 ng/mL) was lower than in Caucasians (40.2 ± 12.6 ng/mL) and Latino-Americans (36.2 ± 15.8 ng/mL).
- Mean AUC0-inf tended to be lower in African-Americans (203 ± 115 ng·hr/mL) than Caucasians (344 ± 186 ng·hr/mL) and Latino-Americans (274 ± 150 ng·hr/mL).
- The mean (± SD) absolute oral bioavailability (F) in African-Americans (12 ± 4.5%) and Latino-Americans (14 ± 7.4%) was lower than in Caucasians (19 ± 5.8%).
- There was no significant difference in mean terminal half-life among the three ethnic groups (range from approximately 25 to 30 hours).

Male and Female Patients
A formal trial to evaluate the effect of gender on tacrolimus pharmacokinetics has not been conducted; however, there was no difference in total mg daily dosages between male and female patients receiving ASTAGRAF XL in the kidney transplant trials. A retrospective comparison of pharmacokinetics in healthy subjects, and in kidney transplant patients indicated no gender-based differences.

Drug Interaction Studies
Because tacrolimus is metabolized mainly by CYP3A enzymes, drugs or substances known to inhibit these enzymes and/or are known CYP3A substrates may increase tacrolimus whole blood concentrations. Drugs known to induce CYP3A enzymes may decrease tacrolimus whole blood concentrations [see Warnings and Precautions (5.10) and Drug Interactions (7.2)].

Figures 1 and 2 summarize the PK data from drug interaction studies of ASTAGRAF XL or tacrolimus immediate‑release capsules. These studies assessed the effect of co-administered drugs on tacrolimus PK in healthy subjects. Dosing adjustments, when using drugs that inhibit or increase CYP3A enzymes, may be necessary [see Drug Interactions (7.2)].

Figure 1: Effect of Co-administered Drugs on the Pharmacokinetics of Tacrolimus (when Given as ASTAGRAF XL)

Figure 2: Effect of Co-administered Drugs on the Pharmacokinetics of Tacrolimus (when Given as Immediate-Release Tacrolimus)

Other Drug Interaction Studies
2. Caspofungin (see complete prescribing information for CANCIDAS): Caspofungin reduced the blood AUC0-12 of tacrolimus by approximately 20%, peak blood concentration (Cmax) by 16%, and 12-hour blood concentration (C12hr) by 26% in healthy adult subjects when tacrolimus (2 doses of 0.1 mg/kg 12 hours apart) was administered on the 10th day of CANCIDAS 70 mg daily, as compared to results from a control period in which tacrolimus was administered alone [see Drug Interactions (7.2)]. The mechanism of interaction has not been confirmed.

13 NONCLINICAL TOXICOLOGY

13.1 Carcinogenesis, Mutagenesis, Impairment of Fertility

Carcinogenesis
Carcinogenicity studies were conducted in male and female rats and mice. In the 80-week mouse oral study and in the 104-week rat oral study, no relationship of tumor incidence to tacrolimus dosage was found. The highest dose used in the mouse was 3 mg/kg/day (0.49 times the AUC at the maximum clinical dose of 0.2 mg/kg/day) and in the rat was 5 mg/kg/day (0.14 times the AUC at the maximum clinical dose of 0.2 mg/kg/day) [see Warnings and Precautions (5.1)].

A 104-week dermal carcinogenicity study was performed in mice with tacrolimus ointment (0.03%-3%), equivalent to tacrolimus doses of 1.1-118 mg/kg/day or 3.3-354 mg/m^2/day. In the study, the incidence of skin tumors was minimal and the topical application of tacrolimus was not associated with skin tumor formation under ambient room lighting. However, a statistically significant elevation in the incidence of pleomorphic lymphoma in high-dose male (25/50) and female animals (27/50), and in the incidence of undifferentiated lymphoma in high-dose female animals (13/50), was noted in the mouse dermal carcinogenicity study. Lymphomas were noted in the mouse dermal carcinogenicity study at a daily dose of 3.5 mg/kg (0.1% tacrolimus ointment; 2.4-fold the human exposure in stable adult kidney transplant patients > 6 months post-transplant). No drug-related tumors were noted in the mouse dermal carcinogenicity study at a daily dose of 1.1 mg/kg (0.03% tacrolimus ointment). The relevance of topical administration of tacrolimus in the setting of systemic tacrolimus use is unknown.

The implications of these carcinogenicity studies are limited; doses of tacrolimus were administered that likely induced immunosuppression in these animals, impairing their immune system’s ability to inhibit unrelated carcinogenesis.

Mutagenesis
No evidence of genotoxicity was seen in bacterial (Salmonella and E. coli) or mammalian (Chinese hamster lung-derived cells) in vitro assays of mutagenicity, the in vitro CHO/HGPRT assay of mutagenicity, or in vivo clastogenicity assays performed in mice; tacrolimus did not cause unscheduled DNA synthesis in rodent hepatocytes.

Impairment of Fertility
Tacrolimus subcutaneously administered to male rats at paternally toxic doses of 2 mg/kg/day [1.6 times the maximum recommended clinical dose (0.2 mg/kg/day) on a mg/m^2 basis] or 3 mg/kg/day (2.4 times the maximum recommended clinical dose) resulted in a dose-related decrease in sperm count.

Tacrolimus administered orally at 1.0 mg/kg (0.8 times the maximum clinical dose) to male and female rats, prior to and during mating, as well as to dams during gestation and lactation, was associated with embryolethality and adverse effects on female reproduction. Effects on female reproductive function (parturition) and embryolethal effects were indicated by a higher rate of pre- and post-implantation loss and increased numbers of undelivered and nonviable pups. When administered at 3.2 mg/kg (2.6 times the maximum clinical dose range based on body surface area), tacrolimus was associated with maternal and paternal toxicity as well as reproductive toxicity including marked adverse effects on estrus cycles, parturition, pup viability, and pup malformations.

14 CLINICAL STUDIES

14.1 ASTAGRAF XL with Basiliximab Induction

Study 1 was a 12-month, randomized, open-label trial of ASTAGRAF XL (N=214) compared to active-control of tacrolimus (Prograf) immediate-release (N=212), conducted primarily in the U.S. in patients who were a recipient of a primary or retransplanted non-HLA-identical living or deceased donor kidney transplant. All patients received basiliximab induction and concomitant mycophenolate mofetil (MMF) and corticosteroids. The study population was 17 to 77 years of age, the mean age was 48 years; 64% were male and 36% were female; 73% were Caucasian, 22% were African-American, 2% were Asian, and 3% were categorized as other races. Living donors provided 49% of the organs and 51% of patients received a kidney transplant from a deceased donor with a mean cold ischemia time of 19 hours. The most frequent diseases leading to transplantation were balanced between the groups and included nephrosclerosis/hypertensive nephropathy, diabetic nephropathy, glomerulonephritis, and polycystic kidney disease. In the study, 97% of patients had no previous transplant and 3% had a previous transplant.

Study Medications
ASTAGRAF XL or Control [Prograf (tacrolimus) capsules]
The initial dose of ASTAGRAF XL was administered prior to reperfusion or within 48 hours after completion of the transplant procedure. The protocol-defined initial post-operative daily doses were 0.15 to 0.20 mg per kg given as a single dose in the morning for ASTAGRAF XL and 0.075 to 0.10 mg per kg twice daily for control. The ASTAGRAF XL and control dosage was then adjusted on the basis of safety and efficacy and a target whole blood tacrolimus trough concentration range of 7 to 16 ng/mL for the first 90 days post-transplant and 5 to 15 ng/mL thereafter.

The average recorded starting tacrolimus daily dose, given any time up to day 2 post-transplant, was higher for ASTAGRAF XL than for control (0.14 mg per kg per day versus 0.10 mg per kg per day). Thereafter, to achieve comparable mean tacrolimus trough concentrations, on average 15% higher total mean daily doses of tacrolimus were required for ASTAGRAF XL than for control.

Tacrolimus whole blood trough concentrations were monitored on Days 3, 7, 10, 14, and 21, then Months 1, 2, 4, 6, 8, 10, and 12. Table 10 shows the tacrolimus whole blood trough concentrations measured at protocol-specified time points for ASTAGRAF XL. Approximately 80% of ASTAGRAF XL-treated patients maintained tacrolimus whole trough blood concentrations between 5 to 17 ng/mL during months 1 through 2 and between 4 to 12 ng/mL from months 3 through 12.

Table 10: Observed Tacrolimus Whole Blood Trough Concentrations in ASTAGRAF XL-Treated Kidney Transplant Patients in Study 1

Scheduled Visit | Tacrolimus Whole Blood Trough Concentrations (ng/mL) [Immunoassay was used in most laboratories.]; [Median (10th to 90th Percentile)]
Day 3 | 9.6 (4.9 to 20.2)
Day 7 | 9.1 (4.4 to 16.8)
Day 14 | 10.0 (5.7 to 16.9)
Month 1 | 10.5 (5.6 to 17.1)
Month 2 | 9.4 (6.1 to 14.2)
Month 6 | 7.7 (4.4 to 11.5)
Month 12 | 7.2 (3.8 to 10.4)

African-American patients required higher ASTAGRAF XL dosages to attain similar trough concentrations as Caucasian patients (see Table 11).

Table 11: ASTAGRAF XL Dosages and Mean Whole Blood Trough Concentrations in African-American and Caucasian Kidney Transplant Patients in Study 1
Time After Transplant | Caucasian Patients; N=160 |  | African-American Patients; N=41
Time After Transplant | Dose; (mg/kg) | Mean Trough; Concentration; (ng/mL) | Dose; (mg/kg) | Mean Trough; Concentration; (ng/mL)
Day 7 | 0.14 | 10.65 | 0.14 | 7.78
Month 1 | 0.14 | 11.11 | 0.17 | 10.92
Month 6 | 0.10 | 7.95 | 0.13 | 8.42
Month 12 | 0.09 | 7.53 | 0.12 | 7.33

MMF
The initial dose of MMF was 1 gram administered orally or intravenously prior to or within 48 hours of completion of the transplant procedure. Subsequent MMF was administered orally 1 gram twice daily or up to 1.5 grams twice daily in African-American patients. Dose-equivalent three times daily or four times daily dosing was permitted if MMF tolerability was a concern.

The MMF dosages administered by time period in ASTAGRAF XL-treated patients are shown in Table 12. The MMF dosage was reduced to less than 2 grams per day by month 12 in 56% of ASTAGRAF XL-treated patients. Approximately 57% of the MMF dose reductions were because of adverse reactions in the ASTAGRAF XL group [see Adverse Reactions (6.1)].

Table 12: Proportion of Patients Who Received 2 grams (or less than or more than 2 grams) of MMF by Time Period in ASTAGRAF XL-Treated Patients in Study 1
Time period; (Days) | Patients on MMF | Time-averaged MMF dosagea
Time period; (Days) | N | Less than; 2 grams per day | 2 grams per; day | Greater than; 2 grams per day
1-30 | 211 | 30% | 64% | 6%
31-90 | 208 | 38% | 57% | 5%
91-180 | 205 | 49% | 48% | 3%
181-365 | 201 | 51% | 47% | 3%
a Time-averaged MMF dosage is the total MMF dosage per day divided by the duration of treatment. A time-averaged MMF dosage of 2 grams per day means that the MMF dosage was not reduced in those patients during the time period.

Basiliximab Induction
All patients were administered 2 doses of basiliximab induction therapy (20 mg intravenously) with the first dose on day 0 before skin closure and the second dose between days 3 and 5.

Steroids
All patients were administered an intravenous bolus of 500 to 1000 mg of methylprednisolone (or an equivalent steroid dose) on day 0 followed by oral administration of 200 mg methylprednisolone (or an equivalent dose of steroid) on day 1 and subsequent tapering to achieve a targeted mean prednisone dose of 5 to 10 mg/day after the first 3 months.

Efficacy Results
The efficacy failure rate, defined as the percentage of patients with biopsy-proven acute rejection (BPAR), graft failure, death, and/or lost to follow at 12 months, is shown in Table 13 for the intent-to-treat population, as well as the rates of the individual events.

Table 13: Incidence of BPAR, Graft Loss, Death or Lost to Follow-up at 12 Months in Kidney Transplant Patients in Study 1
 | ASTAGRAF XL + MMF,; steroids, basiliximab induction (N=214) | Prograf + MMF,; steroids, basiliximab; induction (N=212)
Efficacy Failure | 30 (14.0%) | 32 (15.1%)
Treatment Difference (95% CIa) | -1.1% (-7.8%, +5.6%)
Efficacy Failure Endpoints
Biopsy-Proven Acute Rejection | 22 (10.3%) | 16 (7.5%)
Graft Loss | 5 (2.3%) | 9 (4.2%)
Death | 3 (1.4%) | 9 (4.2%)
Lost to follow-up | 3 (1.4%) | 4 (1.9%)
a 95% confidence interval calculated using normal approximation.

Glomerular Filtration Rate
The estimated mean glomerular filtration rates, using the Modification of Diet in Renal Disease (MDRD) formula, by treatment group at Month 12 in the intent-to-treat population is shown in Table 14.

Table 14: Estimated Glomerular Filtration Rate (mL/min/1.73m^2) by MDRD Formula at 12 Months Post-Transplant in Study 1
 | ASTAGRAF XL + MMF,; steroids, basiliximab; induction; (N=201) | Prograf + MMF, steroids, basiliximab; induction; (N=202)
Month 1 Baseline Mean (SD); Month 12 LOCFa; Mean (Standard deviation); Mean Difference XL minus; Prograf (tacrolimus; immediate-release)b | 56 (20); 58 (21); +2.3 (-1.2, +5.8) | 56 (21); 56 (23)
a Last observation carried forward (LOCF); patients who died, lost the graft, or were lost to follow-up are imputed as zeroes.
b Results from analysis of covariance model with Month 1 baseline as a covariate.

14.2 Clinical Study of ASTAGRAF XL without Induction

Study 2 was a 12-month, randomized, double-blind trial of ASTAGRAF XL (N=331) compared to active control of tacrolimus (Prograf) immediate-release (N=336), in non-U.S. patients who received a primary or retransplanted non-HLA-identical living or deceased donor kidney transplant. This trial was designed to remain double-blind until the last patient enrolled had completed 24 weeks on study treatment. Patients with a high immunologic risk defined as a panel reactive antibody (PRA) grade > 50% in the previous 6 months and/or with a previous graft survival of less than 12 months due to immunologic reasons were excluded, as were patients of donor kidneys with cold ischemia time > 30 hours, or donor kidneys from a non heart-beating donor. The patient treatment assignments remained blinded for 12 months for 96% of the patients participating in the trial.

All patients received concomitant MMF and corticosteroids without induction. The population was 18 to 65 years of age; the mean age was 48 years; 63% of the study population was male; 82% were Caucasian, 5% were African-American, 2% were Asian, and 11% were categorized as other races. Living donors provided 27% of the organs and 73% of patients received a kidney transplant from a deceased donor with a mean cold ischemia time of 17 hours. The most frequent diseases leading to transplantation were balanced between the groups and included nephrosclerosis/hypertensive nephropathy, diabetic nephropathy, glomerulonephritis, and polycystic kidney disease.

Study Medication
ASTAGRAF XL or Control [Prograf (tacrolimus) capsules]

The protocol-specified initial preoperative dose for both ASTAGRAF XL and control was 0.1 mg per kg given orally in one dose within 12 hours prior to reperfusion, given at any time of the day. The initial post-operative tacrolimus daily dose (0.2 mg per kg per day) was given orally in one dose, preferably in the morning for ASTAGRAF XL, and was given as 0.1 mg/kg twice daily for control. Subsequent doses of ASTAGRAF XL and control were adjusted on the basis of clinical evidence of efficacy, occurrence of adverse events and according to whole blood tacrolimus trough concentration target ranges of 10 to 15 ng/mL for the first 28 days post-transplant, 5 to 15 ng/mL from Day 29 to Day 168, 5 to 10 ng/mL thereafter.

The actual tacrolimus doses on day 0 (0.1 mg per kg per day preoperative) and day 1 (0.2 mg per kg per day post-operative) were comparable between ASTAGRAF XL and control. Thereafter, to achieve comparable mean tacrolimus trough concentrations, on average, 25% higher total mean daily doses of tacrolimus were required for ASTAGRAF XL than for control.

Tacrolimus whole blood trough concentrations were monitored on Days 1, 3, 7, 14, then Months 1, 2, 3, 6, 11, 12, and then every 3 months.

Table 15 shows the tacrolimus whole blood trough concentrations measured at protocol-specified time points for ASTAGRAF XL. Approximately 80% of ASTAGRAF XL-treated patients maintained tacrolimus whole trough blood concentrations between 6 to 20 ng/mL during months 1 through 2, and between 6 to 14 ng/mL from months 3 through 12.

Table 15: Observed Tacrolimus Whole Blood Trough Concentrations for ASTAGRAF XL Kidney Transplant Patients Evaluated in Study 2
Scheduled Visit | Tacrolimus Whole Blood Trough Concentrations (ng/mL) [Immunoassay was used in most laboratories.]; [Median (10th to 90th Percentile)]
Day 3 | 13.8 (6.5 to 25.5)
Day 7 | 10.1 (5.5 to 17.3)
Day 14 | 10.8 (6.7 to 17.9)
Month 1 | 12.0 (7.5 to 17.6)
Month 2 | 11.1 (6.6 to 17.3)
Month 6 | 9.2 (5.7 to 13.5)
Month 12 | 8.0 (5.1 to 13.8)

MMF
The initial dose of MMF was 1 gram orally twice daily starting preoperatively and given for the first 14 days of the study. Thereafter the MMF dose was reduced to 0.5 grams twice daily to be maintained throughout the study.

The MMF dosages administered by time period in ASTAGRAF XL-treated patients are shown in Table 16. The MMF dosage was reduced to 0.5 grams twice daily starting after day 14 in the majority of patients.

Table 16: Distribution (%) of ASTAGRAF XL-Treated Patients by Average Daily Dosage of MMF Received by Time Period in Study 2
Time period; (Days) | Patients on; MMF | Time-averaged MMF dosagea, b
Time period; (Days) | N | Less than 1 gram; per day | 1 gram to less than 2 grams per day | 2 grams per; day
1-30 | 331 | 1% | 78% | 21%
31-90 | 303 | 8% | 87% | 6%
91-180 | 281 | 12% | 85% | 3%
181-365 | 258 | 15% | 83% | 2%
a Time-averaged MMF dosage is the total MMF dosage per day divided by the duration of treatment. A time-averaged MMF dosage of 2 grams per day means that the MMF dosage was not reduced in those patients during the time period.
b One patient had a time-averaged dose during the first and last period of > 2 gm/day.

Steroids
An intravenous (IV) bolus of up to 1000 mg methylprednisolone (or equivalent) was administered perioperatively (Day 0) with a second IV bolus of 125 mg being administered 1 day after reperfusion (Day 1). On Day 2, oral prednisone was started at 20 mg per day. Thereafter, the dose of oral prednisone (or equivalent) was tapered to a dose of 0 to 5 mg/day.

No Antibody Induction
Antibody induction therapy was not allowed.

Efficacy Results
The efficacy failure rate, defined as the percentage of patients with biopsy-proven acute rejection (BPAR), graft failure, death, and/or lost to follow at 12 months, is shown in Table 17 for the intent-to-treat population, as well as the rates of the individual events. About 1% of randomized patients were not transplanted and were not included in the ITT analysis.

Table 17: Incidence of BPAR, Graft Loss, Death or Lost to Follow-up at 12 Months in Kidney Transplant Patients in Study 2
 | ASTAGRAF XL + MMF and steroids; (N=331) | Prograf + MMF and steroids; (N=336)
Efficacy Failure | 93 (28.1%) | 78 (23.2%)
Treatment Difference (95% CIa) | +4.9% (-1.7%, +11.5%)
Efficacy Failure Endpoints
Biopsy-Proven Acute Rejection | 68 (20.5%) | 54 (16.1%)
Graft loss | 28 (8.5%) | 24 (7.1%)
Death | 10 (3%) | 8 (2.4%)
Lost to follow-up | 4 (1.2%) | 7 (2.1%)
a 95% confidence interval calculated using normal approximation.

Glomerular Filtration Rate
The estimated mean glomerular filtration rates, using the Modification of Diet in Renal Disease (MDRD) formula, by treatment group at Month 12 in the intent-to-treat population in Study 2 is shown in Table 18.

Table 18: Estimated Glomerular Filtration Rate (mL/min/1.73m^2) by MDRD Formula at 12 Months Post-Kidney Transplant in Study 2
 | ASTAGRAF XL + MMF; and steroids; (N=287) | Prograf + MMF and steroids; (N=300)
Month 1 Baseline Mean (SD); Month 12 LOCFa; Mean (Standard deviation); Mean Difference ASTAGRAF XL minus; Prograf (tacrolimus immediate-release)b | 51 (19); 52 (20); -1.8 (-4.6, +0.8) | 52 (20); 55 (19)
a Last observation carried forward (LOCF); patients who died, lost the graft or were lost to follow-up are imputed as zeroes.
b Results from analysis of covariance model with Month 1 baseline as a covariate.

16 HOW SUPPLIED/STORAGE AND HANDLING

ASTAGRAF XL (tacrolimus) extended-release capsules are supplied in short, square bottles (see Table 19).

Table 19: Strengths of ASTAGRAF XL
0.5 mg | Oblong capsule with a light yellow cap and orange body. Capsule is branded with red “ 647” on capsule body and “0.5 mg” on the capsule cap. The bottle packaging is branded with a brown stripe.; - 30-count in short, square bottles with a brown cap (NDC 0469-0647-73)
1 mg | Oblong capsule with a white cap and orange body. Capsule is branded with red “ 677” on capsule body and “1 mg” on the capsule cap. The bottle packaging is branded with a blue stripe.; - 30-count in short, square bottles with a blue cap (NDC 0469-0677-73)
5 mg | Oblong capsule with a grayish-red cap and orange body. Capsule is branded with red “ 687” on capsule body and “5 mg” on the capsule cap. The bottle packaging is branded with an orange stripe.; - 30-count in short, square bottles with an orange cap (NDC 0469-0687-73)

Store and Dispense

Store at 25°C (77°F); excursions permitted to 15°C to 30°C (59°F to 86°F) [see USP Controlled Room Temperature].

17 PATIENT COUNSELING INFORMATION

Advise the patient to read the FDA-approved patient labeling (Medication Guide).

17.1 Administration

Advise patients or caregivers to:

- Inspect their ASTAGRAF XL medicine when they receive a new prescription and before taking it. If the appearance of the capsule is not the same as usual, or if dosage instructions have changed, advise patients to contact their healthcare provider as soon as possible to make sure that they have the right medicine. Other tacrolimus products cannot be substituted for ASTAGRAF XL [see Warnings and Precautions (5.4)].
- Take ASTAGRAF XL at the same time every day to achieve consistent blood concentrations.
- Take ASTAGRAF XL in the morning, on an empty stomach at least 1 hour before or at least 2 hours after breakfast, to achieve maximum possible blood concentrations of the drug.
- Swallow capsule whole with liquid. Do not chew, divide or crush capsule.
- Avoid alcoholic beverages, grapefruit, and grapefruit juice while on ASTAGRAF XL [see Dosage and Administration (2.1) and Drug Interactions (7.2)].
- Take a missed dose of ASTAGRAF XL as soon as possible but not more than 14 hours after the scheduled time (i.e., for a missed 8 AM dose, take by 10 PM). Beyond the 14-hour timeframe, instruct the patient to wait until the usual scheduled time the following morning to take the next scheduled dose. Do not take 2 doses at the same time.

17.2 Development of Lymphoma and Other Malignancies

Inform patients that they are at an increased risk of developing lymphomas and other malignancies, particularly of the skin, due to immunosuppression. Advise patients to limit exposure to sunlight and ultraviolet (UV) light by wearing protective clothing and using a broad spectrum sunscreen with a high protection factor [see Warnings and Precautions (5.1)].

17.3 Increased Risk of Infection

Inform patients that they are at an increased risk of developing a variety of infections, including opportunistic infections, due to immunosuppression and to contact their physician if they develop any symptoms of infection such as fever, sweats or chills, cough or flu-like symptoms, muscle aches, or warm, red, painful areas of the skin [see Boxed Warning and Warnings and Precautions (5.2)].

17.4 New Onset Diabetes after Transplant

Inform patients that ASTAGRAF XL can cause diabetes mellitus and should be advised to contact their physician if they develop frequent urination, increased thirst or hunger [see Warnings and Precautions (5.5)].

17.5 Nephrotoxicity

Inform patients that ASTAGRAF XL can have toxic effects on the kidney that should be monitored. Advise patients to attend all visits and complete all blood tests ordered by their medical team [see Warnings and Precautions (5.6)].

17.6 Neurotoxicity

Inform patients that they are at risk of developing adverse neurologic reactions including seizure, altered mental status, and tremor. Advise patients to contact their physician should they develop vision changes, delirium, or tremors [see Warnings and Precautions (5.7)].

17.7 Hyperkalemia

Inform patients that ASTAGRAF XL can cause hyperkalemia. Monitoring of potassium levels may be necessary, especially with concomitant use of other drugs known to cause hyperkalemia [see Warnings and Precautions (5.8)].

17.8 Hypertension

Inform patients that ASTAGRAF XL can cause high blood pressure which may require treatment with anti-hypertensive therapy [see Warnings and Precautions (5.9)]. Advise patients to monitor their blood pressure.

17.9 Thrombotic Microangiopathy

Inform patients that ASTAGRAF XL can cause blood clotting problems. The risk of this occurring increases when patients take ASTAGRAF XL and sirolimus or everolimus concomitantly, or when patients develop certain infections. Advise them to seek medical attention promptly if they develop fever, petequiae or bruises, fatigue, confusion, jaundice, oliguria [see Warnings and Precautions (5.14)].

17.10 Drug Interactions

Instruct patients to tell their healthcare providers when they start or stop taking any medicines, including prescription and nonprescription medicines, herbal and dietary supplements. Some medications could alter tacrolimus concentrations in the blood and thus may require the adjustment of the dosage of ASTAGRAF XL. Advise patients to avoid grapefruit, grapefruit juice and alcoholic beverages [see Warnings and Precautions (5.10, 5.15) and Drug Interactions (7)].

17.11 Pregnancy, Lactation and Infertility

Inform women of childbearing potential that ASTAGRAF XL can harm the fetus. Instruct male and female patients to discuss with their healthcare provider family planning options including appropriate contraception. Also, discuss with pregnant patients the risks and benefits of breastfeeding their infant [see Use in Specific Populations (8.1, 8.2, 8.3)].

Encourage female transplant patients who become pregnant and male patients who have fathered a pregnancy, exposed to immunosuppressants including tacrolimus, to enroll in the voluntary Transplantation Pregnancy Registry International. To enroll or register, patients can call the toll free number 1-877-955-6877 or https://www.transplantpregnancyregistry.org/ [see Use in Specific Populations (8.1)].

Based on animal studies, ASTAGRAF XL may affect fertility in males and females [see Nonclinical Toxicology (13.1)].

17.12 Immunizations

Inform patients that ASTAGRAF XL can interfere with the usual response to immunizations and that they should avoid live vaccines [see Warnings and Precautions (5.12)].

Product of Japan

Distributed by:
Astellas Pharma US, Inc.
Northbrook, IL 60062

ASTAGRAF XL® is a registered trademark of Astellas Pharma Inc.
Prograf ® is a registered trademark of Astellas Pharma Inc.

398977-AST

MEDICATION GUIDE

ASTAGRAF XL® [as' tah graf ex el']

(tacrolimus)

extended-release capsules

Read this Medication Guide before you start taking ASTAGRAF XL and each time you get a refill. There may be new information. This information does not take the place of talking with your healthcare provider about your medical condition or your treatment. If you have any questions about ASTAGRAF XL, ask your healthcare provider or pharmacist.

What is the most important information I should know about ASTAGRAF XL?

ASTAGRAF XL can cause serious side effects, including:

- Increased risk of cancer. People who take ASTAGRAF XL have an increased risk of getting some kinds of cancer, including skin and lymph gland cancer (lymphoma).
- Increased risk of infection. ASTAGRAF XL is a medicine that affects your immune system. ASTAGRAF XL can lower the ability of your immune system to fight infections. Serious infections can happen in people receiving ASTAGRAF XL that can cause death. Call your healthcare provider right away if you have symptoms of an infection such as:

- fever
- sweats or chills

- cough or flu-like symptoms
- muscle aches

- warm, red, or painful areas on your skin

- Increased risk of death in females who have had a liver transplant. You should not take ASTAGRAF XL if you have had a liver transplant without talking to your healthcare provider.

What is ASTAGRAF XL?

- ASTAGRAF XL is a prescription medicine used with other medicines to help prevent organ rejection in people who have had a kidney transplant.
- ASTAGRAF XL is an extended-release capsule and is not the same as tacrolimus immediate-release capsules, tacrolimus for oral suspension or tacrolimus extended-release tablets. Your healthcare provider should decide what medicine is right for you.

Who should not take ASTAGRAF XL?

- Do not take ASTAGRAF XL if you are allergic to tacrolimus or any of the ingredients in ASTAGRAF XL. See the end of this leaflet for a complete list of ingredients in ASTAGRAF XL.

What should I tell my healthcare provider before taking ASTAGRAF?

Before you take ASTAGRAF XL tell your healthcare provider if you:

- plan to receive any live vaccines. Ask your healthcare provider if you are not sure if your vaccine is a live vaccine.
- have or have had liver, kidney, or heart problems or any other medical conditions.
- are pregnant or plan to become pregnant. ASTAGRAF XL may harm your unborn baby.
  - If you are able to become pregnant, you should use effective birth control before and during treatment with ASTAGRAF XL. Talk to your healthcare provider before starting treatment with ASTAGRAF XL about birth control methods that may be right for you.
  - Males who have female partners that are able to become pregnant should also use effective birth control before and during treatment with ASTAGRAF XL. Talk to your healthcare provider before starting treatment with ASTAGRAF XL about birth control methods that may be right for you.
  - There is a pregnancy registry for females who become pregnant and males who have fathered a pregnancy during treatment with ASTAGRAF XL. The purpose of this registry is to collect information about your health and of your baby. To enroll in this voluntary registry, call 1-877-955-6877 or go to https://www.transplantpregnancyregistry.org/.
- are breastfeeding or plan to breastfeed. ASTAGRAF XL passes into your breast milk. You and your healthcare provider should decide if you will breastfeed while taking ASTAGRAF XL.

Tell your healthcare provider about all the medicines you take, including prescription and over-the-counter medicines, vitamins, natural, herbal or nutritional supplements. ASTAGRAF XL may affect the way other medicines work, and other medicines may affect how ASTAGRAF XL works.

Especially tell your healthcare provider if you take:

- sirolimus (RAPAMUNE): You should not take ASTAGRAF XL if you take sirolimus
- cyclosporine (GENGRAF, NEORAL, and SANDIMMUNE)
- medicines called aminoglycosides that are used to treat bacterial infections
- ganciclovir (CYTOVENE IV, VALCYTE)
- amphotericin B (ABELCET, AMBISOME)
- cisplatin
- antiviral medicines called nucleoside reverse transcriptase inhibitors
- antiviral medicines called protease inhibitors
- water pill (diuretic)
- medicine to treat high blood pressure
- nelfinavir (VIRACEPT)
- telaprevir (INCIVEK)
- boceprevir
- ritonavir (KALETRA, NORVIR, TECHNIVIE, VIEKIRA PAK, VIEKIRA XR)
- letermovir (PREVYMIS)
- ketoconazole
- itraconazole (ONMEL, SPORANOX)
- voriconazole (VFEND)
- caspofungin (CANCIDAS)
- clarithromycin (BIAXIN, BIAXIN XL, PREVPAC)
- rifampin (RIFADIN, RIFAMATE, RIFATER, RIMACTANE)
- rifabutin (MYCOBUTIN)
- amiodarone (NEXTERONE, PACERONE)
- cannabidiol (EPIDIOLEX)

Ask your healthcare provider or pharmacist if you are not sure if you take any of the medicines listed above.

ASTAGRAF XL may affect the way other medicines work, and other medicines may affect how ASTAGRAF XL works.

Know the medicines you take. Keep a list of your medicines and show it to your healthcare provider and pharmacist when you get a new medicine.

How should I take ASTAGRAF XL?

- Take ASTAGRAF XL exactly as your healthcare provider tells you to take it.
- Your healthcare provider may change your dose if needed. Do not stop taking or change your dose of ASTAGRAF XL without talking to your healthcare provider.
- Take ASTAGRAF XL capsules whole. Do not break, crush, chew, or dissolve ASTAGRAF XL capsules before swallowing. If you cannot swallow ASTAGRAF XL capsules whole, tell your healthcare provider.
- Take ASTAGRAF XL at the same time each morning, preferably on an empty stomach at least 1 hour before, or at least 2 hours after, you have eaten a meal.
- If you miss your dose of ASTAGRAF XL, it should be taken as soon as possible, but no longer than 14 hours after your regularly scheduled time. If it is longer than 14 hours, the missed dose should be skipped and the next dose should be taken the following morning at your regularly scheduled time. Do not take 2 doses at the same time.
- If you take too much ASTAGRAF XL, call your healthcare provider or go to the nearest hospital emergency room right away.

What should I avoid while taking ASTAGRAF XL?

- Live vaccines such as flu vaccine through your nose, measles, mumps, rubella, polio by mouth, BCG (TB vaccine), yellow fever, chicken pox (varicella) or typhoid.
- Exposure to sunlight and UV light such as tanning machines. Wear protective clothing and use a sunscreen.
- You should not eat grapefruit or drink grapefruit juice while taking ASTAGRAF XL.
- You should not drink alcohol when taking ASTAGRAF XL.

What are the possible side effects of ASTAGRAF XL?

ASTAGRAF XL may cause serious side effects, including:

- See “What is the most important information I should know about ASTAGRAF XL?”
- Problems from medication errors such as graft rejection and other serious reactions. People who take ASTAGRAF XL have sometimes been given the wrong medicine because some medicines have the same ingredient (tacrolimus) as ASTAGRAF XL. Serious reactions have happened including graft rejection. Check your ASTAGRAF XL when you get a new prescription to make sure you have received the right medicine.
  - Call your healthcare provider right away if you think you were given the wrong medicine.
  - Ask your healthcare provider or pharmacist if you are not sure what ASTAGRAF XL should look like.
- high blood sugar (diabetes). Your healthcare provider may do certain tests to check for diabetes while you take ASTAGRAF XL. Call your healthcare provider right away if you have:

- frequent urination
- increased thirst or hunger
- blurred vision

- confusion
- drowsiness
- loss of appetite

- fruity smell on your breath
- nausea, vomiting, or stomach pain

- kidney problems. Kidney problems are serious and common side effects of ASTAGRAF XL. Your healthcare provider may do certain tests to check your kidney function while you take ASTAGRAF XL.
- nervous system problems. Nervous system problems are a serious and common side effect of ASTAGRAF XL. Call your healthcare provider or go to the nearest hospital emergency room right away if you get any of these symptoms while taking ASTAGRAF XL. These could be signs of serious nervous system problems:

- confusion
- changes in alertness
- muscle tremors

- numbness and tingling
- headache

- seizures
- vision changes

- high levels of potassium in your blood. Your healthcare provider may do certain tests to check your potassium level while you take ASTAGRAF XL.
- high blood pressure. High blood pressure is a serious and common side effect of ASTAGRAF XL. Your healthcare provider will monitor your blood pressure while you take ASTAGRAF XL and may ask you to check your blood pressure at home.
- changes in the electrical activity of your heart (QT prolongation).
- severe low blood cell count (anemia).
- blood clotting problems: Tell your healthcare provider right away if you have fever and bruising under the skin that may appear as red dots, with or without unexplained tiredness, confusion, yellowing of the skin or eyes, decreased urination. When taken with sirolimus or everolimus, the risk of developing these symptoms may increase.

The most common side effects of ASTAGRAF XL are diarrhea, constipation, nausea, swelling of the hands, ankles, or legs, and tremors (shaking of the body).

These are not all the possible side effects of ASTAGRAF XL. For more information, ask your healthcare provider or pharmacist.

Call your healthcare provider for medical advice about side effects. You may report side effects to FDA at 1-800-FDA-1088.

How should I store ASTAGRAF XL?

- Store ASTAGRAF XL at room temperature between 68°F to 77°F (20°C to 25°C).
- Safely throw away medicine that is out of date or no longer needed.
- Keep ASTAGRAF XL and all medicines out of reach of children.

General information about the safe and effective use of ASTAGRAF XL.

- Medicines are sometimes prescribed for purposes other than those listed in a Medication Guide. Do not use ASTAGRAF XL for a condition for which it was not prescribed. Do not give ASTAGRAF XL to other people, even if they have the same symptoms that you have. It may harm them.
- This Medication Guide summarizes the most important information about ASTAGRAF XL. If you would like more information, talk to your healthcare provider. You can ask your pharmacist or healthcare provider for information about ASTAGRAF XL that is written for health professionals.

What are the ingredients in ASTAGRAF XL?

Active ingredient: tacrolimus.

Inactive ingredients:

- The capsule contains: ethylcellulose NF, hypromellose USP, magnesium stearate NF, and lactose monohydrate NF
- The capsule shell contains: gelatin NF, titanium dioxide USP, ferric oxide NF, and sodium lauryl sulfate

Distributed by: Astellas Pharma US, Inc., Northbrook, IL 60062

ASTAGRAF XL® is a registered trademark of Astellas Pharma Inc.

398977-AST-MG

This Medication Guide has been approved by the U.S. Food and Drug Administration. Issued: 08/2023

PACKAGE/LABEL PRINCIPAL DISPLAY PANEL – 0.5 mg carton label

NDC 0469-0647-73

Astagraf XL®
(tacrolimus extended-release capsules)

0.5 mg

ONCE-DAILY

30 Capsules

Rx Only

PACKAGE/LABEL PRINCIPAL DISPLAY PANEL – 1 mg carton label

NDC 0469-0677-73

Astagraf XL®
(tacrolimus extended-release capsules)

1 mg

ONCE-DAILY

30 Capsules

Rx Only

PACKAGE/LABEL PRINCIPAL DISPLAY PANEL – 5 mg carton label

NDC 0469-0687-73

Astagraf XL®
(tacrolimus extended-release capsules)

5 mg

ONCE-DAILY

30 Capsules

Rx Only